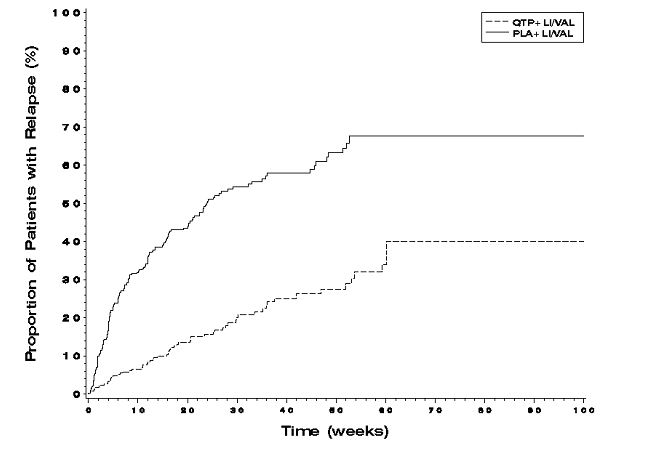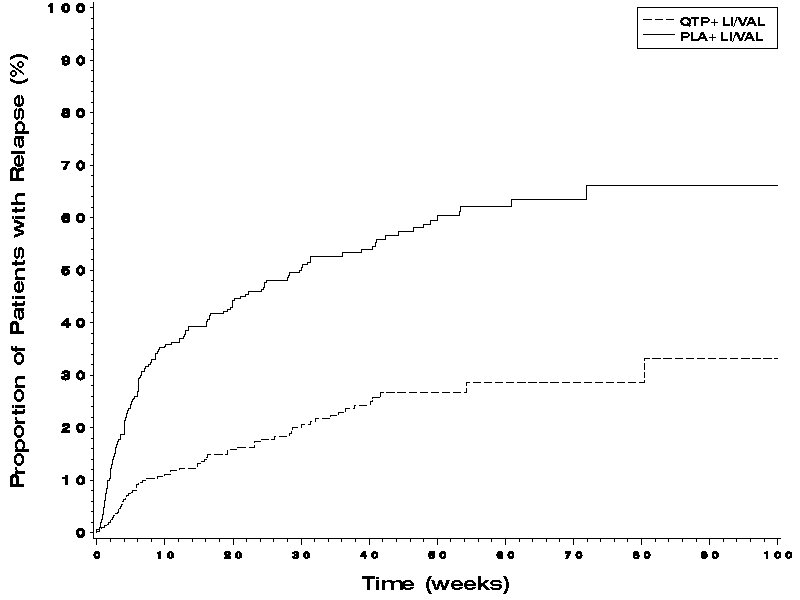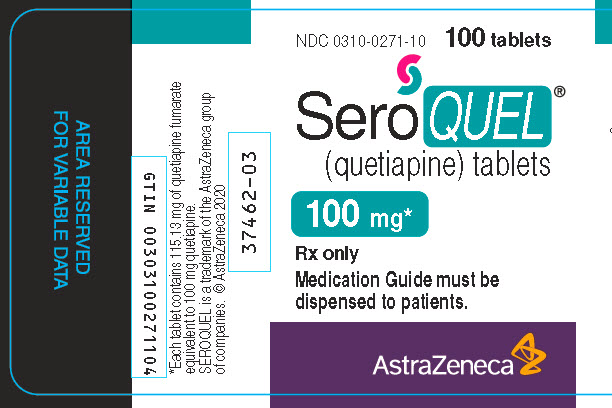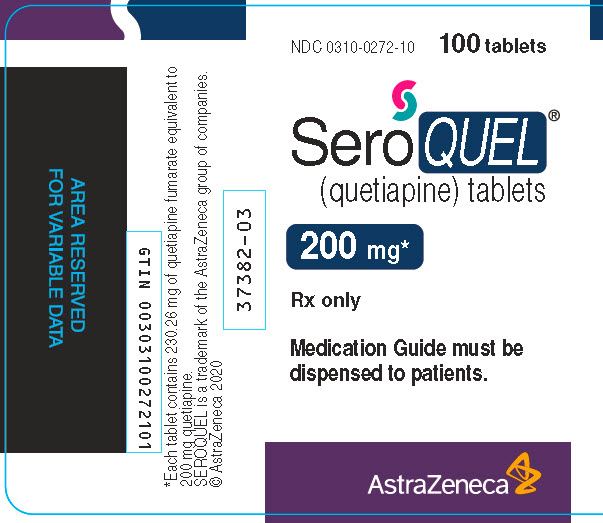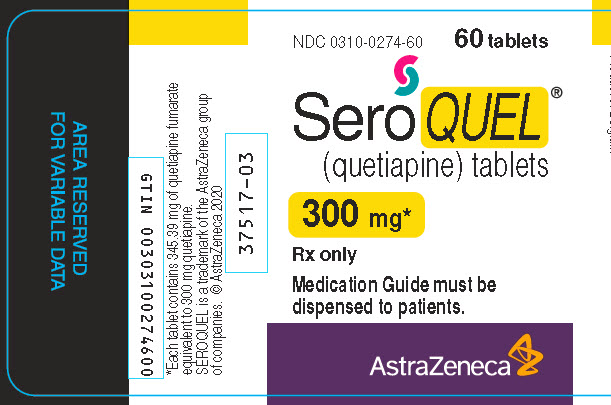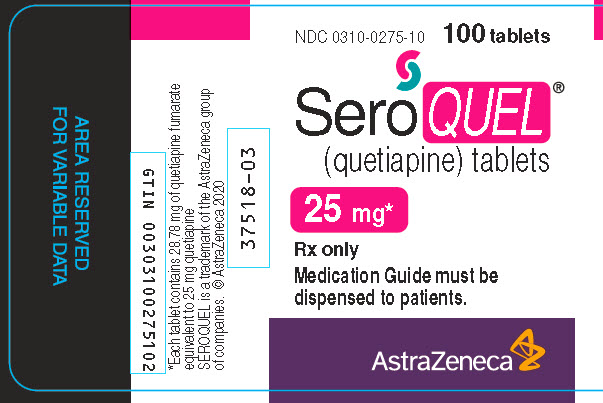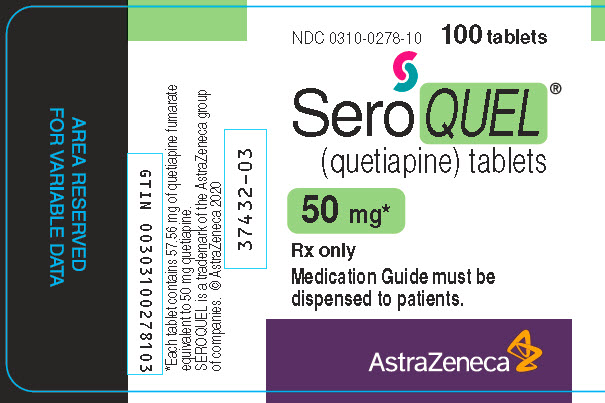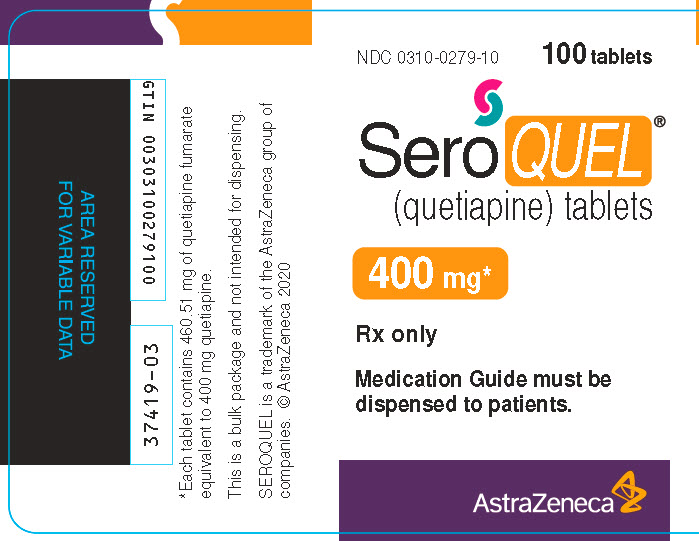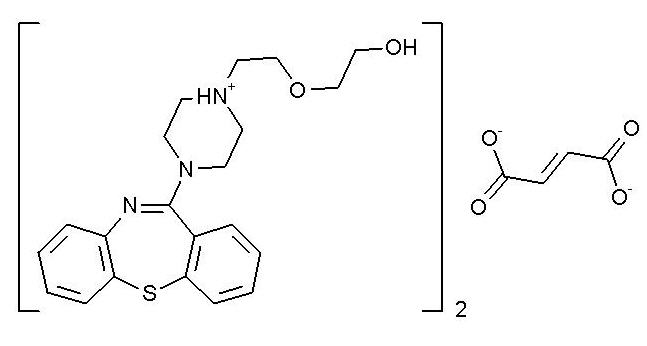 DRUG LABEL: SEROQUEL
NDC: 0310-0275 | Form: TABLET, FILM COATED
Manufacturer: AstraZeneca Pharmaceuticals LP
Category: prescription | Type: HUMAN PRESCRIPTION DRUG LABEL
Date: 20250122

ACTIVE INGREDIENTS: QUETIAPINE FUMARATE 25 mg/1 1
INACTIVE INGREDIENTS: POVIDONE, UNSPECIFIED; DIBASIC CALCIUM PHOSPHATE DIHYDRATE; MICROCRYSTALLINE CELLULOSE; SODIUM STARCH GLYCOLATE TYPE A POTATO; MAGNESIUM STEARATE; HYPROMELLOSE, UNSPECIFIED; POLYETHYLENE GLYCOL, UNSPECIFIED; TITANIUM DIOXIDE; FERRIC OXIDE RED; FERRIC OXIDE YELLOW; LACTOSE MONOHYDRATE; WATER

HIGHLIGHTS OF PRESCRIBING INFORMATION

These highlights do not include all the information needed to use SEROQUEL safely and effectively. See full prescribing information for SEROQUEL.
SEROQUEL® (quetiapine) tablets, for oral use
Initial U.S. Approval: 1997

RECENT MAJOR CHANGES

WARNINGS AND PRECAUTIONS (5.15) 1/2025

WARNING: INCREASED MORTALITY IN ELDERLY PATIENTS WITH DEMENTIA-RELATED PSYCHOSIS; and SUICIDAL THOUGHTS AND BEHAVIORS

See full prescribing information for complete boxed warning.

Increased Mortality in Elderly Patients with Dementia-Related Psychosis

- Elderly patients with dementia-related psychosis treated with antipsychotic drugs are at an increased risk of death. SEROQUEL is not approved for elderly patients with dementia-related psychosis (5.1)

Suicidal Thoughts and Behaviors

- Increased risk of suicidal thoughts and behavior in children, adolescents and young adults taking antidepressants (5.2)
- Monitor for worsening and emergence of suicidal thoughts and behaviors (5.2)

1 INDICATIONS AND USAGE

SEROQUEL is an atypical antipsychotic indicated for the treatment of:

- Schizophrenia (1.1)
- Bipolar I disorder manic episodes (1.2)
- Bipolar disorder, depressive episodes (1.2)

2 DOSAGE AND ADMINISTRATION

- SEROQUEL can be taken with or without food (2.1)

Indication | Initial Dose | Recommended Dose | Maximum Dose
Schizophrenia - Adults (2.2) | 25 mg twice daily | 150-750 mg/day | 750 mg/day
Schizophrenia - Adolescents (13-17 years) (2.2) | 25 mg twice daily | 400-800 mg/day | 800 mg/day
Bipolar Mania - Adults Monotherapy or as an adjunct to lithium or divalproex (2.2) | 50 mg twice daily | 400-800 mg/day | 800 mg/day
Bipolar Mania - Children and Adolescents (10-17 years), Monotherapy (2.2) | 25 mg twice daily | 400-600 mg/day | 600 mg/day
Bipolar Depression - Adults (2.2) | 50 mg once daily at bedtime | 300 mg/day | 300 mg/day

- Geriatric Use: Consider a lower starting dose (50 mg/day), slower titration and careful monitoring during the initial dosing period in the elderly (2.3, 8.5)
- Hepatic Impairment: Lower starting dose (25 mg/day) and slower titration may be needed (2.4, 8.7, 12.3)

3 DOSAGE FORMS AND STRENGTHS

Tablets: 25 mg, 50 mg, 100 mg, 200 mg, 300 mg, and 400 mg (3)

4 CONTRAINDICATIONS

Known hypersensitivity to SEROQUEL or any components in the formulation. (4)

5 WARNINGS AND PRECAUTIONS

- Cerebrovascular Adverse Reactions: Increased incidence of cerebrovascular adverse reactions (e.g., stroke, transient ischemic attack) has been seen in elderly patients with dementia-related psychoses treated with atypical antipsychotic drugs (5.3)
- Neuroleptic Malignant Syndrome (NMS): Manage with immediate discontinuation and close monitoring (5.4)
- Metabolic Changes: Atypical antipsychotics have been associated with metabolic changes. These metabolic changes include hyperglycemia, dyslipidemia, and weight gain (5.5)
  ∘ Hyperglycemia and Diabetes Mellitus: Monitor patients for symptoms of hyperglycemia including polydipsia, polyuria, polyphagia, and weakness. Monitor glucose regularly in patients with diabetes or at risk for diabetes
  ∘ Dyslipidemia: Undesirable alterations have been observed in patients treated with atypical antipsychotics. Appropriate clinical monitoring is recommended, including fasting blood lipid testing at the beginning of, and periodically, during treatment
  ∘ Weight Gain: Gain in body weight has been observed; clinical monitoring of weight is recommended
- Tardive Dyskinesia: Discontinue if clinically appropriate (5.6)
- Hypotension: Use with caution in patients with known cardiovascular or cerebrovascular disease (5.7)
- Increased Blood Pressure in Children and Adolescents: Monitor blood pressure at the beginning of, and periodically during treatment in children and adolescents (5.9)
- Leukopenia, Neutropenia and Agranulocytosis: Monitor complete blood count frequently during the first few months of treatment in patients with a pre-existing low white cell count or a history of leukopenia/neutropenia and discontinue SEROQUEL at the first sign of a decline in WBC in absence of other causative factors (5.10)
- Cataracts: Lens changes have been observed in patients during long-term quetiapine treatment. Lens examination is recommended when starting treatment and at 6-month intervals during chronic treatment (5.11)
- Anticholinergic(antimuscarinic) Effects: Use with caution with other anticholinergic drugs and in patients with urinary retention, prostatic hypertrophy, or constipation (5.20)

6 ADVERSE REACTIONS

- Most common adverse reactions (incidence ≥5% and twice placebo): Adults: somnolence, dry mouth, dizziness, constipation, asthenia, abdominal pain, postural hypotension, pharyngitis, weight gain, lethargy, ALT increased, dyspepsia (6.1)
- Children and Adolescents: somnolence, dizziness, fatigue, increased appetite, nausea, vomiting, dry mouth, tachycardia, weight increased (6.1)

To report SUSPECTED ADVERSE REACTIONS, contact AstraZeneca at 1-800-236-9933 or FDA at 1-800-FDA-1088 or www.fda.gov/medwatch.

7 DRUG INTERACTIONS

- Concomitant use of strong CYP3A4 inhibitors: Reduce quetiapine dose to one sixth when coadministered with strong CYP3A4 inhibitors (e.g., ketoconazole, ritonavir) (2.5, 7.1, 12.3)
- Concomitant use of strong CYP3A4 inducers: Increase quetiapine dose up to 5 fold when used in combination with a chronic treatment (more than 7-14 days) of potent CYP3A4 inducers (e.g., phenytoin, rifampin, St. John’s wort) (2.6, 7.1, 12.3)
- Discontinuation of strong CYP3A4 inducers: Reduce quetiapine dose by 5-fold within 7-14 days of discontinuation of CYP3A4 inducers (2.6, 7.1, 12.3)

8 USE IN SPECIFIC POPULATIONS

- Pregnancy: May cause extrapyramidal and/or withdrawal symptoms in neonates with third trimester exposure. (8.1)

FULL PRESCRIBING INFORMATION

WARNING: INCREASED MORTALITY IN ELDERLY PATIENTS WITH DEMENTIA-RELATED PSYCHOSIS; and SUICIDAL THOUGHTS AND BEHAVIORS

Increased Mortality in Elderly Patients with Dementia-Related Psychosis

Elderly patients with dementia-related psychosis treated with antipsychotic drugs are at an increased risk of death [see Warnings and Precautions (5.1)]. SEROQUEL is not approved for the treatment of patients with dementia-related psychosis [see Warnings and Precautions (5.1)].

Suicidal Thoughts and Behaviors

Antidepressants increased the risk of suicidal thoughts and behavior in children, adolescents, and young adults in short-term studies. These studies did not show an increase in the risk of suicidal thoughts and behavior with antidepressant use in patients over age 24; there was a reduction in risk with antidepressant use in patients aged 65 and older [see Warnings and Precautions (5.2)].

In patients of all ages who are started on antidepressant therapy, monitor closely for worsening, and for emergence of suicidal thoughts and behaviors. Advise families and caregivers of the need for close observation and communication with the prescriber [see Warnings and Precautions (5.2)].

SEROQUEL is not approved for use in pediatric patients under ten years of age [see Use in Specific Populations (8.4)].

1 INDICATIONS AND USAGE

1.1 Schizophrenia

SEROQUEL is indicated for the treatment of schizophrenia. The efficacy of SEROQUEL in schizophrenia was established in three 6-week trials in adults and one 6-week trial in adolescents (13-17 years). The effectiveness of SEROQUEL for the maintenance treatment of schizophrenia has not been systematically evaluated in controlled clinical trials [see Clinical Studies (14.1)].

1.2 Bipolar Disorder

SEROQUEL is indicated for the acute treatment of manic episodes associated with bipolar I disorder, both as monotherapy and as an adjunct to lithium or divalproex. Efficacy was established in two 12-week monotherapy trials in adults, in one 3-week adjunctive trial in adults, and in one 3-week monotherapy trial in pediatric patients (10-17 years) [see Clinical Studies (14.2)].

SEROQUEL is indicated as monotherapy for the acute treatment of depressive episodes associated with bipolar disorder. Efficacy was established in two 8-week monotherapy trials in adult patients with bipolar I and bipolar II disorder [see Clinical Studies (14.2)].

SEROQUEL is indicated for the maintenance treatment of bipolar I disorder, as an adjunct to lithium or divalproex. Efficacy was established in two maintenance trials in adults. The effectiveness of SEROQUEL as monotherapy for the maintenance treatment of bipolar disorder has not been systematically evaluated in controlled clinical trials [see Clinical Studies (14.2)].

1.3 Special Considerations in Treating Pediatric Schizophrenia and Bipolar I Disorder

Pediatric schizophrenia and bipolar I disorder are serious mental disorders, however, diagnosis can be challenging. For pediatric schizophrenia, symptom profiles can be variable, and for bipolar I disorder, patients may have variable patterns of periodicity of manic or mixed symptoms. It is recommended that medication therapy for pediatric schizophrenia and bipolar I disorder be initiated only after a thorough diagnostic evaluation has been performed and careful consideration given to the risks associated with medication treatment. Medication treatment for both pediatric schizophrenia and bipolar I disorder is indicated as part of a total treatment program that often includes psychological, educational and social interventions.

2 DOSAGE AND ADMINISTRATION

2.1 Important Administration Instructions

SEROQUEL can be taken with or without food.

2.2 Recommended Dosing

The recommended initial dose, titration, dose range and maximum SEROQUEL dose for each approved indication is displayed in Table 1. After initial dosing, adjustments can be made upwards or downwards, if necessary, depending upon the clinical response and tolerability of the patient [see Clinical Studies (14.1 and 14.2)].

Table 1: Recommended Dosing for SEROQUEL
Indication | Initial Dose and Titration | Recommended Dose | Maximum Dose
Schizophrenia - Adults | Day 1: 25 mg twice daily.; Increase in increments of 25 mg-50 mg divided two or three times on Days 2 and 3 to range of 300-400 mg by Day 4.; Further adjustments can be made in increments of 25–50 mg twice a day, in intervals of not less than 2 days. | 150-750 mg/day | 750 mg/day
Schizophrenia - Adolescents (13-17 years) | Day 1: 25 mg twice daily.; Day 2: Twice daily dosing totaling 100 mg.; Day 3: Twice daily dosing totaling 200 mg.; Day 4: Twice daily dosing totaling 300 mg.; Day 5: Twice daily dosing totaling 400 mg.; Further adjustments should be in increments no greater than 100 mg/day within the recommended dose range of 400-800 mg/day.; Based on response and tolerability, may be administered three times daily. | 400-800 mg/day | 800 mg/day
Schizophrenia - Maintenance | Not applicable. | 400-800 mg/day | 800 mg/day
Bipolar Mania - Adults Monotherapy or as an adjunct to lithium or divalproex | Day 1: Twice daily dosing totaling 100 mg.; Day 2: Twice daily dosing totaling 200 mg.; Day 3: Twice daily dosing totaling 300 mg.; Day 4: Twice daily dosing totaling 400 mg.; Further dosage adjustments up to 800 mg/day by Day 6 should be in increments of no greater than 200 mg/day. | 400-800 mg/day | 800 mg/day
Bipolar Mania - Children and Adolescents (10 to 17 years),; Monotherapy | Day 1: 25 mg twice daily.; Day 2: Twice daily dosing totaling 100 mg.; Day 3: Twice daily dosing totaling 200 mg.; Day 4: Twice daily dosing totaling 300 mg.; Day 5: Twice daily dosing totaling 400 mg.; Further adjustments should be in increments no greater than 100 mg/day within the recommended dose range of 400-600 mg/day.; Based on response and tolerability, may be administered three times daily. | 400-600 mg/day | 600 mg/day
Bipolar Depression - Adults | Administer once daily at bedtime.; Day 1: 50 mg; Day 2: 100 mg; Day 3: 200 mg; Day 4: 300 mg | 300 mg/day | 300 mg/day
Bipolar I Disorder Maintenance Therapy - Adults | Administer twice daily totaling 400-800 mg/day as adjunct to lithium or divalproex. Generally, in the maintenance phase, patients continued on the same dose on which they were stabilized. | 400-800 mg/day | 800 mg/day

Maintenance Treatment for Schizophrenia and Bipolar I Disorder

Maintenance Treatment – Patients should be periodically reassessed to determine the need for maintenance treatment and the appropriate dose for such treatment [see Clinical Studies (14.2)].

2.3 Dose Modifications in Elderly Patients

Consideration should be given to a slower rate of dose titration and a lower target dose in the elderly and in patients who are debilitated or who have a predisposition to hypotensive reactions [see Clinical Pharmacology (12.3)]. When indicated, dose escalation should be performed with caution in these patients.

Elderly patients should be started on SEROQUEL 50 mg/day and the dose can be increased in increments of 50 mg/day depending on the clinical response and tolerability of the individual patient.

2.4 Dose Modifications in Hepatically Impaired Patients

Patients with hepatic impairment should be started on 25 mg/day. The dose should be increased daily in increments of 25 mg/day - 50 mg/day to an effective dose, depending on the clinical response and tolerability of the patient.

2.5 Dose Modifications when used with CYP3A4 Inhibitors

SEROQUEL dose should be reduced to one sixth of original dose when co-medicated with a potent CYP3A4 inhibitor (e.g., ketoconazole, itraconazole, indinavir, ritonavir, nefazodone, etc.). When the CYP3A4 inhibitor is discontinued, the dose of SEROQUEL should be increased by 6-fold [see Clinical Pharmacology (12.3) and Drug Interactions (7.1)].

2.6 Dose Modifications when used with CYP3A4 Inducers

SEROQUEL dose should be increased up to 5-fold of the original dose when used in combination with a chronic treatment (e.g., greater than 7-14 days) of a potent CYP3A4 inducer (e.g., phenytoin, carbamazepine, rifampin, avasimibe, St. John’s wort etc.). The dose should be titrated based on the clinical response and tolerability of the individual patient. When the CYP3A4 inducer is discontinued, the dose of SEROQUEL should be reduced to the original level within 7-14 days [see Clinical Pharmacology (12.3) and Drug Interactions (7.1)].

2.7 Re-initiation of Treatment in Patients Previously Discontinued

Although there are no data to specifically address re-initiation of treatment, it is recommended that when restarting therapy of patients who have been off SEROQUEL for more than one-week, the initial dosing schedule should be followed. When restarting patients who have been off SEROQUEL for less than one-week, gradual dose escalation may not be required and the maintenance dose may be re-initiated.

2.8 Switching from Antipsychotics

There are no systematically collected data to specifically address switching patients with schizophrenia from antipsychotics to SEROQUEL, or concerning concomitant administration with antipsychotics. While immediate discontinuation of the previous antipsychotic treatment may be acceptable for some patients with schizophrenia, more gradual discontinuation may be most appropriate for others. In all cases, the period of overlapping antipsychotic administration should be minimized. When switching patients with schizophrenia from depot antipsychotics, if medically appropriate, initiate SEROQUEL therapy in place of the next scheduled injection. The need for continuing existing EPS medication should be re-evaluated periodically.

3 DOSAGE FORMS AND STRENGTHS

- 25 mg tablets are peach, round, biconvex, film-coated tablets, identified with 'SEROQUEL' and ‘25’ on one side and plain on the other side
- 50 mg tablets are white, round, biconvex, film-coated tablets, identified with 'SEROQUEL' and ‘50’ on one side and plain on the other side
- 100 mg tablets are yellow, round, biconvex, film-coated tablets, identified with 'SEROQUEL' and ‘100’ on one side and plain on the other side
- 200 mg tablets are white, round, biconvex, film-coated tablets, identified with ‘SEROQUEL’ and ‘200’ on one side and plain on the other side
- 300 mg tablets are white, capsule-shaped, biconvex, film-coated tablets, intagliated with ‘SEROQUEL’ on one side and ‘300’ on the other side
- 400 mg tablets are yellow, capsule-shaped, biconvex, film-coated tablets, intagliated with ‘SEROQUEL’ on one side and ‘400’ on the other side

4 CONTRAINDICATIONS

Hypersensitivity to quetiapine or to any excipients in the SEROQUEL formulation. Anaphylactic reactions have been reported in patients treated with SEROQUEL.

5 WARNINGS AND PRECAUTIONS

5.1 Increased Mortality in Elderly Patients with Dementia-Related Psychosis

Elderly patients with dementia-related psychosis treated with antipsychotic drugs are at an increased risk of death. Analysis of 17 placebo-controlled trials (modal duration of 10 weeks), largely in patients taking atypical antipsychotic drugs, revealed a risk of death in drug-treated patients of between 1.6 to 1.7 times the risk of death in placebo-treated patients. Over the course of a typical 10-week controlled trial, the rate of death in drug-treated patients was about 4.5%, compared to a rate of about 2.6% in the placebo group. Although the causes of death were varied, most of the deaths appeared to be either cardiovascular (e.g., heart failure, sudden death) or infectious (e.g., pneumonia) in nature. Observational studies suggest that, similar to atypical antipsychotic drugs, treatment with conventional antipsychotic drugs may increase mortality. The extent to which the findings of increased mortality in observational studies may be attributed to the antipsychotic drug as opposed to some characteristic(s) of the patients is not clear. SEROQUEL is not approved for the treatment of patients with dementia-related psychosis [see Boxed Warning].

5.2 Suicidal Thoughts and Behaviors in Adolescents and Young Adults

Patients with major depressive disorder (MDD), both adult and pediatric, may experience worsening of their depression and/or the emergence of suicidal ideation and behavior (suicidality) or unusual changes in behavior, whether or not they are taking antidepressant medications, and this risk may persist until significant remission occurs. Suicide is a known risk of depression and certain other psychiatric disorders, and these disorders themselves are the strongest predictors of suicide. There has been a long-standing concern, however, that antidepressants may have a role in inducing worsening of depression and the emergence of suicidality in certain patients during the early phases of treatment. Pooled analyses of short-term placebo-controlled trials of antidepressant drugs (SSRIs and others) showed that these drugs increase the risk of suicidal thinking and behavior (suicidality) in children, adolescents, and young adults (ages 18-24) with major depressive disorder (MDD) and other psychiatric disorders. Short-term studies did not show an increase in the risk of suicidality with antidepressants compared to placebo in adults beyond age 24; there was a reduction with antidepressants compared to placebo in adults aged 65 and older.

The pooled analyses of placebo-controlled trials in children and adolescents with MDD, obsessive-compulsive disorder (OCD), or other psychiatric disorders included a total of 24 short-term trials of 9 antidepressant drugs in over 4400 patients. The pooled analyses of placebo-controlled trials in adults with MDD or other psychiatric disorders included a total of 295 short-term trials (median duration of 2 months) of 11 antidepressant drugs in over 77,000 patients. There was considerable variation in risk of suicidality among drugs, but a tendency toward an increase in the younger patients for almost all drugs studied. There were differences in absolute risk of suicidality across the different indications, with the highest incidence in MDD. The risk differences (drug vs. placebo), however, were relatively stable within age strata and across indications. These risk differences (drug-placebo difference in the number of cases of suicidality per 1000 patients treated) are provided in Table 2.

Table 2: Drug-Placebo Difference in Number of Cases of Suicidality per 1000 Patients Treated
Age Range | Drug-Placebo Difference in Number of Cases of Suicidality per 1000 Patients Treated
 | Increases Compared to Placebo
<18 | 14 additional cases
18-24 | 5 additional cases
 | Decreases Compared to Placebo
25-64 | 1 fewer case
≥65 | 6 fewer cases

No suicides occurred in any of the pediatric trials. There were suicides in the adult trials, but the number was not sufficient to reach any conclusion about drug effect on suicide.

It is unknown whether the suicidality risk extends to longer-term use, i.e., beyond several months. However, there is substantial evidence from placebo-controlled maintenance trials in adults with depression that the use of antidepressants can delay the recurrence of depression.

All patients being treated with antidepressants for any indication should be monitored appropriately and observed closely for clinical worsening, suicidality, and unusual changes in behavior, especially during the initial few months of a course of drug therapy, or at times of dose changes, either increases or decreases.

The following symptoms, anxiety, agitation, panic attacks, insomnia, irritability, hostility, aggressiveness, impulsivity, akathisia (psychomotor restlessness), hypomania, and mania, have been reported in adult and pediatric patients being treated with antidepressants for major depressive disorder as well as for other indications, both psychiatric and non-psychiatric. Although a causal link between the emergence of such symptoms and either the worsening of depression and/or the emergence of suicidal impulses has not been established, there is concern that such symptoms may represent precursors to emerging suicidality.

Consideration should be given to changing the therapeutic regimen, including possibly discontinuing the medication, in patients whose depression is persistently worse, or who are experiencing emergent suicidality or symptoms that might be precursors to worsening depression or suicidality, especially if these symptoms are severe, abrupt in onset, or were not part of the patient's presenting symptoms.

Families and caregivers of patients being treated with antidepressants for major depressive disorder or other indications, both psychiatric and non-psychiatric, should be alerted about the need to monitor patients for the emergence of agitation, irritability, unusual changes in behavior, and the other symptoms described above, as well as the emergence of suicidality, and to report such symptoms immediately to healthcare providers. Such monitoring should include daily observation by families and caregivers. Prescriptions for SEROQUEL should be written for the smallest quantity of tablets consistent with good patient management, in order to reduce the risk of overdose.

Screening Patients for Bipolar Disorder: A major depressive episode may be the initial presentation of bipolar disorder. It is generally believed (though not established in controlled trials) that treating such an episode with an antidepressant alone may increase the likelihood of precipitation of a mixed/manic episode in patients at risk for bipolar disorder. Whether any of the symptoms described above represent such a conversion is unknown. However, prior to initiating treatment with an antidepressant, including SEROQUEL, patients with depressive symptoms should be adequately screened to determine if they are at risk for bipolar disorder; such screening should include a detailed psychiatric history, including a family history of suicide, bipolar disorder, and depression.

5.3 Cerebrovascular Adverse Reactions, Including Stroke, in Elderly Patients with Dementia-Related Psychosis

In placebo-controlled trials with risperidone, aripiprazole, and olanzapine in elderly subjects with dementia, there was a higher incidence of cerebrovascular adverse reactions (cerebrovascular accidents and transient ischemic attacks) including fatalities compared to placebo-treated subjects. SEROQUEL is not approved for the treatment of patients with dementia-related psychosis [see also Boxed Warning and Warnings and Precautions (5.1)].

5.4 Neuroleptic Malignant Syndrome (NMS)

A potentially fatal symptom complex sometimes referred to as Neuroleptic Malignant Syndrome (NMS) has been reported in association with administration of antipsychotic drugs, including SEROQUEL. Rare cases of NMS have been reported with SEROQUEL. Clinical manifestations of NMS are hyperpyrexia, muscle rigidity, altered mental status, and evidence of autonomic instability (irregular pulse or blood pressure, tachycardia, diaphoresis, and cardiac dysrhythmia). Additional signs may include elevated creatinine phosphokinase, myoglobinuria (rhabdomyolysis) and acute renal failure.

The diagnostic evaluation of patients with this syndrome is complicated. In arriving at a diagnosis, it is important to exclude cases where the clinical presentation includes both serious medical illness (e.g., pneumonia, systemic infection, etc.) and untreated or inadequately treated extrapyramidal signs and symptoms (EPS). Other important considerations in the differential diagnosis include central anticholinergic toxicity, heat stroke, drug fever, and primary central nervous system (CNS) pathology.

The management of NMS should include: 1) immediate discontinuation of antipsychotic drugs and other drugs not essential to concurrent therapy; 2) intensive symptomatic treatment and medical monitoring; and 3) treatment of any concomitant serious medical problems for which specific treatments are available. There is no general agreement about specific pharmacological treatment regimens for NMS.

If a patient requires antipsychotic drug treatment after recovery from NMS, the potential reintroduction of drug therapy should be carefully considered. The patient should be carefully monitored since recurrences of NMS have been reported.

5.5 Metabolic Changes

Atypical antipsychotic drugs have been associated with metabolic changes that include hyperglycemia/diabetes mellitus, dyslipidemia, and body weight gain. While all of the drugs in the class have been shown to produce some metabolic changes, each drug has its own specific risk profile. In some patients, a worsening of more than one of the metabolic parameters of weight, blood glucose, and lipids was observed in clinical studies. Changes in these metabolic profiles should be managed as clinically appropriate.

Hyperglycemia and Diabetes Mellitus

Hyperglycemia, in some cases extreme and associated with ketoacidosis or hyperosmolar coma or death, has been reported in patients treated with atypical antipsychotics, including quetiapine. Assessment of the relationship between atypical antipsychotic use and glucose abnormalities is complicated by the possibility of an increased background risk of diabetes mellitus in patients with schizophrenia and the increasing incidence of diabetes mellitus in the general population. Given these confounders, the relationship between atypical antipsychotic use and hyperglycemia-related adverse reactions is not completely understood. However, epidemiological studies suggest an increased risk of hyperglycemia-related adverse reactions in patients treated with the atypical antipsychotics. Precise risk estimates for hyperglycemia-related adverse reactions in patients treated with atypical antipsychotics are not available.

Patients with an established diagnosis of diabetes mellitus who are started on atypical antipsychotics should be monitored regularly for worsening of glucose control. Patients with risk factors for diabetes mellitus (e.g., obesity, family history of diabetes) who are starting treatment with atypical antipsychotics should undergo fasting blood glucose testing at the beginning of treatment and periodically during treatment. Any patient treated with atypical antipsychotics should be monitored for symptoms of hyperglycemia including polydipsia, polyuria, polyphagia, and weakness. Patients who develop symptoms of hyperglycemia during treatment with atypical antipsychotics should undergo fasting blood glucose testing. In some cases, hyperglycemia has resolved when the atypical antipsychotic was discontinued; however, some patients required continuation of anti-diabetic treatment despite discontinuation of the suspect drug.

Adults:

Table 3: Fasting Glucose - Proportion of Patients Shifting to ≥126 mg/dL in Short-Term (≤12 weeks) Placebo-Controlled Studies [Includes SEROQUEL and SEROQUEL XR data.]
Laboratory Analyte | Category Change (At Least Once) from Baseline | Treatment Arm | N | Patients; n (%)
Fasting; Glucose | Normal to High; (<100 mg/dL to; ≥126 mg/dL) | Quetiapine | 2907 | 71 (2.4%)
Fasting; Glucose | Normal to High; (<100 mg/dL to; ≥126 mg/dL) | Placebo | 1346 | 19 (1.4%)
Fasting; Glucose | Borderline to High; (≥100 mg/dL and <126 mg/dL to; ≥126 mg/dL) | Quetiapine | 572 | 67 (11.7%)
Fasting; Glucose | Borderline to High; (≥100 mg/dL and <126 mg/dL to; ≥126 mg/dL) | Placebo | 279 | 33 (11.8%)

In a 24-week trial (active-controlled, 115 patients treated with SEROQUEL) designed to evaluate glycemic status with oral glucose tolerance testing of all patients, at Week 24 the incidence of a post-glucose challenge glucose level ≥200 mg/dL was 1.7% and the incidence of a fasting blood glucose level ≥126 mg/dL was 2.6%. The mean change in fasting glucose from baseline was 3.2 mg/dL and mean change in 2-hour glucose from baseline was -1.8 mg/dL for quetiapine.

In 2 long-term placebo-controlled randomized withdrawal clinical trials for bipolar I disorder maintenance, mean exposure of 213 days for SEROQUEL (646 patients) and 152 days for placebo (680 patients), the mean change in glucose from baseline was +5.0 mg/dL for SEROQUEL and –0.05 mg/dL for placebo. The exposure-adjusted rate of any increased blood glucose level (≥126 mg/dL) for patients more than 8 hours since a meal (however, some patients may not have been precluded from calorie intake from fluids during fasting period) was 18.0 per 100 patient years for SEROQUEL (10.7% of patients; n=556) and 9.5 for placebo per 100 patient years (4.6% of patients; n=581).

Children and Adolescents:

In a placebo-controlled SEROQUEL monotherapy study of adolescent patients (13–17 years of age) with schizophrenia (6 weeks duration), the mean change in fasting glucose levels for SEROQUEL (n=138) compared to placebo (n=67) was –0.75 mg/dL versus –1.70 mg/dL. In a placebo-controlled SEROQUEL monotherapy study of children and adolescent patients (10–17 years of age) with bipolar mania (3 weeks duration), the mean change in fasting glucose level for SEROQUEL (n=170) compared to placebo (n=81) was 3.62 mg/dL versus –1.17 mg/dL. No patient in either study with a baseline normal fasting glucose level (<100 mg/dL) or a baseline borderline fasting glucose level (≥100 mg/dL and <126 mg/dL) had a blood glucose level of ≥126 mg/dL.

In a placebo-controlled SEROQUEL XR monotherapy study (8 weeks duration) of children and adolescent patients (10-17 years of age) with bipolar depression, in which efficacy was not established, the mean change in fasting glucose levels for SEROQUEL XR (n=60) compared to placebo (n=62) was 1.8 mg/dL versus 1.6 mg/dL. In this study, there were no patients in the SEROQUEL XR or placebo-treated groups with a baseline normal fasting glucose level (<100 mg/dL) that had an increase in blood glucose level >126 mg/dL. There was one patient in the SEROQUEL XR group with a baseline borderline fasting glucose level (>100 mg/dL and <126 mg/dL) who had an increase in blood glucose level of >126 mg/dL compared to zero patients in the placebo group.

Dyslipidemia

Adults:

Table 4 shows the percentage of adult patients with changes in total cholesterol, triglycerides, LDL-cholesterol, and HDL-cholesterol from baseline by indication in clinical trials with SEROQUEL.

Table 4: Percentage of Adult Patients with Shifts in Total Cholesterol, Triglycerides, LDL-Cholesterol, and HDL-Cholesterol from Baseline to Clinically Significant Levels by Indication
Laboratory Analyte | Indication | Treatment Arm | N | Patients; n (%)
Total Cholesterol ≥240 mg/dL | Schizophrenia [6 weeks duration] | SEROQUEL | 137 | 24 (18%)
Total Cholesterol ≥240 mg/dL | Schizophrenia [6 weeks duration] | Placebo | 92 | 6 (7%)
Total Cholesterol ≥240 mg/dL | Bipolar; Depression [8 weeks duration] | SEROQUEL | 463 | 41 (9%)
Total Cholesterol ≥240 mg/dL | Bipolar; Depression [8 weeks duration] | Placebo | 250 | 15 (6%)
Triglycerides ≥200 mg/dL | Schizophrenia | SEROQUEL | 120 | 26 (22%)
Triglycerides ≥200 mg/dL | Schizophrenia | Placebo | 70 | 11 (16%)
Triglycerides ≥200 mg/dL | Bipolar; Depression | SEROQUEL | 436 | 59 (14%)
Triglycerides ≥200 mg/dL | Bipolar; Depression | Placebo | 232 | 20 (9%)
LDL-; Cholesterol; ≥160 mg/dL | Schizophrenia | SEROQUEL | na [Parameters not measured in the SEROQUEL registration studies for schizophrenia.] | na
LDL-; Cholesterol; ≥160 mg/dL | Schizophrenia | Placebo | na | na
LDL-; Cholesterol; ≥160 mg/dL | Bipolar; Depression | SEROQUEL | 465 | 29 (6%)
LDL-; Cholesterol; ≥160 mg/dL | Bipolar; Depression | Placebo | 256 | 12 (5%)
HDL- Cholesterol; ≤40 mg/dL | Schizophrenia | SEROQUEL | na | na
HDL- Cholesterol; ≤40 mg/dL | Schizophrenia | Placebo | na | na
HDL- Cholesterol; ≤40 mg/dL | Bipolar; Depression | SEROQUEL | 393 | 56 (14%)
HDL- Cholesterol; ≤40 mg/dL | Bipolar; Depression | Placebo | 214 | 29 (14%)

Children and Adolescents:

Table 5 shows the percentage of children and adolescents with changes in total cholesterol, triglycerides, LDL-cholesterol, and HDL-cholesterol from baseline in clinical trials with SEROQUEL.

Table 5: Percentage of Children and Adolescents with Shifts in Total Cholesterol, Triglycerides, LDL-Cholesterol, and HDL-Cholesterol from Baseline to Clinically Significant Levels
Laboratory; Analyte | Indication | Treatment Arm | N | Patients; n (%)
Total Cholesterol ≥200 mg/dL | Schizophrenia [13-17 years, 6 weeks duration] | SEROQUEL | 107 | 13 (12%)
Total Cholesterol ≥200 mg/dL | Schizophrenia [13-17 years, 6 weeks duration] | Placebo | 56 | 1 (2%)
Total Cholesterol ≥200 mg/dL | Bipolar Mania [10-17 years, 3 weeks duration] | SEROQUEL | 159 | 16 (10%)
Total Cholesterol ≥200 mg/dL | Bipolar Mania [10-17 years, 3 weeks duration] | Placebo | 66 | 2 (3%)
Triglycerides; ≥150 mg/dL | Schizophrenia | SEROQUEL | 103 | 17 (17%)
Triglycerides; ≥150 mg/dL | Schizophrenia | Placebo | 51 | 4 (8%)
Triglycerides; ≥150 mg/dL | Bipolar Mania | SEROQUEL | 149 | 32 (22%)
Triglycerides; ≥150 mg/dL | Bipolar Mania | Placebo | 60 | 8 (13%)
LDL-Cholesterol ≥130 mg/dL | Schizophrenia | SEROQUEL | 112 | 4 (4%)
LDL-Cholesterol ≥130 mg/dL | Schizophrenia | Placebo | 60 | 1 (2%)
LDL-Cholesterol ≥130 mg/dL | Bipolar Mania | SEROQUEL | 169 | 13 (8%)
LDL-Cholesterol ≥130 mg/dL | Bipolar Mania | Placebo | 74 | 4 (5%)
HDL-Cholesterol ≤40 mg/dL | Schizophrenia | SEROQUEL | 104 | 16 (15%)
HDL-Cholesterol ≤40 mg/dL | Schizophrenia | Placebo | 54 | 10 (19%)
HDL-Cholesterol ≤40 mg/dL | Bipolar Mania | SEROQUEL | 154 | 16 (10%)
HDL-Cholesterol ≤40 mg/dL | Bipolar Mania | Placebo | 61 | 4 (7%)

In a placebo-controlled SEROQUEL XR monotherapy study (8 weeks duration) of children and adolescent patients (10 to 17 years of age) with bipolar depression, in which efficacy was not established, the percentage of children and adolescents with shifts in total cholesterol (≥200 mg/dL), triglycerides (≥150 mg/dL), LDL-cholesterol (≥ 130 mg/dL), and HDL-cholesterol (≤40 mg/dL) from baseline to clinically significant levels were: total cholesterol 8% (7/83) for SEROQUEL XR vs. 6% (5/84) for placebo; triglycerides 28% (22/80) for SEROQUEL XR vs. 9% (7/82) for placebo; LDL-cholesterol 2% (2/86) for SEROQUEL XR vs. 4% (3/85) for placebo and HDL-cholesterol 20% (13/65) for SEROQUEL XR vs. 15% (11/74) for placebo.

Weight Gain

Increases in weight have been observed in clinical trials. Patients receiving quetiapine should receive regular monitoring of weight.

Adults:

In clinical trials with SEROQUEL the following increases in weight have been reported.

Table 6: Proportion of Patients with Weight Gain ≥7% of Body Weight (Adults)
Vital Sign | Indication | Treatment Arm | N | Patients; n (%)
Weight Gain ≥7% of Body Weight | Schizophrenia [up to 6 weeks duration] | SEROQUEL | 391 | 89 (23%)
Weight Gain ≥7% of Body Weight | Schizophrenia [up to 6 weeks duration] | Placebo | 206 | 11 (6%)
Weight Gain ≥7% of Body Weight | Bipolar Mania (monotherapy) [up to 12 weeks duration] | SEROQUEL | 209 | 44 (21%)
Weight Gain ≥7% of Body Weight | Bipolar Mania (monotherapy) [up to 12 weeks duration] | Placebo | 198 | 13 (7%)
Weight Gain ≥7% of Body Weight | Bipolar Mania (adjunct therapy) [up to 3 weeks duration] | SEROQUEL | 196 | 25 (13%)
Weight Gain ≥7% of Body Weight | Bipolar Mania (adjunct therapy) [up to 3 weeks duration] | Placebo | 203 | 8 (4%)
Weight Gain ≥7% of Body Weight | Bipolar Depression [up to 8 weeks duration] | SEROQUEL | 554 | 47 (8%)
Weight Gain ≥7% of Body Weight | Bipolar Depression [up to 8 weeks duration] | Placebo | 295 | 7 (2%)

Children and Adolescents:

In two clinical trials with SEROQUEL, one in bipolar mania and one in schizophrenia, reported increases in weight are included in Table 7.

Table 7: Proportion of Patients with Weight Gain ≥7% of Body Weight (Children and Adolescents)
Vital Sign | Indication | Treatment Arm | N | Patients; n (%)
Weight Gain ≥7% of Body Weight | Schizophrenia [6 weeks duration] | SEROQUEL | 111 | 23 (21%)
Weight Gain ≥7% of Body Weight | Schizophrenia [6 weeks duration] | Placebo | 44 | 3 (7%)
Weight Gain ≥7% of Body Weight | Bipolar Mania [3 weeks duration] | SEROQUEL | 157 | 18 (12%)
Weight Gain ≥7% of Body Weight | Bipolar Mania [3 weeks duration] | Placebo | 68 | 0 (0%)

The mean change in body weight in the schizophrenia trial was 2.0 kg in the SEROQUEL group and -0.4 kg in the placebo group and in the bipolar mania trial, it was 1.7 kg in the SEROQUEL group and 0.4 kg in the placebo group.

In an open-label study that enrolled patients from the above two pediatric trials, 63% of patients (241/380) completed 26 weeks of therapy with SEROQUEL. After 26 weeks of treatment, the mean increase in body weight was 4.4 kg. Forty-five percent of the patients gained ≥7% of their body weight, not adjusted for normal growth. In order to adjust for normal growth over 26 weeks, an increase of at least 0.5 standard deviation from baseline in BMI was used as a measure of a clinically significant change; 18.3% of patients on SEROQUEL met this criterion after 26 weeks of treatment.

In a clinical trial for SEROQUEL XR in children and adolescents (10-17 years of age) with bipolar depression, in which efficacy was not established, the percentage of patients with weight gain ≥7% of body weight at any time was 15% (14/92) for SEROQUEL XR vs. 10% (10/100) for placebo. The mean change in body weight was 1.4 kg in the SEROQUEL XR group vs. 0.6 kg in the placebo group.

When treating pediatric patients with SEROQUEL for any indication, weight gain should be assessed against that expected for normal growth.

5.6 Tardive Dyskinesia

A syndrome of potentially irreversible, involuntary, dyskinetic movements may develop in patients treated with antipsychotic drugs, including quetiapine. Although the prevalence of the syndrome appears to be highest among the elderly, especially elderly women, it is impossible to rely upon prevalence estimates to predict, at the inception of antipsychotic treatment, which patients are likely to develop the syndrome. Whether antipsychotic drug products differ in their potential to cause tardive dyskinesia is unknown.

The risk of developing tardive dyskinesia and the likelihood that it will become irreversible are believed to increase as the duration of treatment and the total cumulative dose of antipsychotic drugs administered to the patient increase. However, the syndrome can develop, although much less commonly, after relatively brief treatment periods at low doses or may even arise after discontinuation of treatment.

Tardive dyskinesia may remit, partially or completely, if antipsychotic treatment is withdrawn. Antipsychotic treatment, itself, however, may suppress (or partially suppress) the signs and symptoms of the syndrome and thereby may possibly mask the underlying process. The effect that symptomatic suppression has upon the long-term course of the syndrome is unknown.

Given these considerations, SEROQUEL should be prescribed in a manner that is most likely to minimize the occurrence of tardive dyskinesia. Chronic antipsychotic treatment should generally be reserved for patients who appear to suffer from a chronic illness that (1) is known to respond to antipsychotic drugs, and (2) for whom alternative, equally effective, but potentially less harmful treatments are not available or appropriate. In patients who do require chronic treatment, the smallest dose and the shortest duration of treatment producing a satisfactory clinical response should be sought. The need for continued treatment should be reassessed periodically.

If signs and symptoms of tardive dyskinesia appear in a patient on SEROQUEL, drug discontinuation should be considered. However, some patients may require treatment with SEROQUEL despite the presence of the syndrome.

5.7 Hypotension

Quetiapine may induce orthostatic hypotension associated with dizziness, tachycardia and, in some patients, syncope, especially during the initial dose-titration period, probably reflecting its α1-adrenergic antagonist properties. Syncope was reported in 1% (28/3265) of the patients treated with SEROQUEL, compared with 0.2% (2/954) on placebo and about 0.4% (2/527) on active control drugs. Orthostatic hypotension, dizziness, and syncope may lead to falls.

SEROQUEL should be used with particular caution in patients with known cardiovascular disease (history of myocardial infarction or ischemic heart disease, heart failure, or conduction abnormalities), cerebrovascular disease or conditions which would predispose patients to hypotension (dehydration, hypovolemia, and treatment with antihypertensive medications). The risk of orthostatic hypotension and syncope may be minimized by limiting the initial dose to 25 mg twice daily [see Dosage and Administration (2.2)]. If hypotension occurs during titration to the target dose, a return to the previous dose in the titration schedule is appropriate.

5.8 Falls

Atypical antipsychotic drugs, including SEROQUEL, may cause somnolence, postural hypotension, motor, and sensory instability, which may lead to falls and, consequently, fractures or other injuries. For patients with diseases, conditions, or medications that could exacerbate these effects, complete fall risk assessments when initiating antipsychotic treatment and recurrently for patients on long-term antipsychotic therapy.

5.9 Increases in Blood Pressure (Children and Adolescents)

In placebo-controlled trials in children and adolescents with schizophrenia (6-week duration) or bipolar mania (3-week duration), the incidence of increases at any time in systolic blood pressure (≥20 mmHg) was 15.2% (51/335) for SEROQUEL and 5.5% (9/163) for placebo; the incidence of increases at any time in diastolic blood pressure (≥10 mmHg) was 40.6% (136/335) for SEROQUEL and 24.5% (40/163) for placebo. In the 26-week open-label clinical trial, one child with a reported history of hypertension experienced a hypertensive crisis. Blood pressure in children and adolescents should be measured at the beginning of, and periodically during treatment.

In a placebo-controlled SEROQUEL XR clinical trial (8 weeks duration) in children and adolescents (10-17 years of age) with bipolar depression, in which efficacy was not established, the incidence of increases at any time in systolic blood pressure (≥20 mmHg) was 6.5% (6/92) for SEROQUEL XR and 6.0% (6/100) for placebo; the incidence of increases at any time in diastolic blood pressure (≥10 mmHg) was 46.7% (43/92) for SEROQUEL XR and 36.0% (36/100) for placebo.

5.10 Leukopenia, Neutropenia, and Agranulocytosis

In clinical trial and postmarketing experience, events of leukopenia/neutropenia have been reported temporally related to atypical antipsychotic agents, including SEROQUEL. Agranulocytosis has been reported.

Agranulocytosis (defined as absolute neutrophil count <500/mm3) has been reported with quetiapine, including fatal cases and cases in patients without pre-existing risk factors. Neutropenia should be considered in patients presenting with infection, particularly in the absence of obvious predisposing factor(s), or in patients with unexplained fever, and should be managed as clinically appropriate.

Possible risk factors for leukopenia/neutropenia include pre-existing low white cell count (WBC) and history of drug induced leukopenia/neutropenia. Patients with a pre-existing low WBC or a history of drug induced leukopenia/neutropenia should have their complete blood count (CBC) monitored frequently during the first few months of therapy and should discontinue SEROQUEL at the first sign of a decline in WBC in absence of other causative factors.

Patients with neutropenia should be carefully monitored for fever or other symptoms or signs of infection and treated promptly if such symptoms or signs occur. Patients with severe neutropenia (absolute neutrophil count <1000/mm3) should discontinue SEROQUEL and have their WBC followed until recovery.

5.11 Cataracts

The development of cataracts was observed in association with quetiapine treatment in chronic dog studies [see Nonclinical Toxicology (13.2)]. Lens changes have also been observed in adults, children, and adolescents during long-term SEROQUEL treatment, but a causal relationship to SEROQUEL use has not been established. Nevertheless, the possibility of lenticular changes cannot be excluded at this time. Therefore, examination of the lens by methods adequate to detect cataract formation, such as slit lamp exam or other appropriately sensitive methods, is recommended at initiation of treatment or shortly thereafter, and at 6-month intervals during chronic treatment.

5.12 QT Prolongation

In clinical trials, quetiapine was not associated with a persistent increase in QT intervals. However, the QT effect was not systematically evaluated in a thorough QT study. In post marketing experience, there were cases reported of QT prolongation in patients who overdosed on quetiapine [see Overdosage (10.1)], in patients with concomitant illness, and in patients taking medicines known to cause electrolyte imbalance or increase QT interval [see Drug Interactions (7.1)].

The use of quetiapine should be avoided in combination with other drugs that are known to prolong QTc including Class 1A antiarrythmics (e.g., quinidine, procainamide) or Class III antiarrythmics (e.g., amiodarone, sotalol), antipsychotic medications (e.g., ziprasidone, chlorpromazine, thioridazine), antibiotics (e.g., gatifloxacin, moxifloxacin), or any other class of medications known to prolong the QTc interval (e.g., pentamidine, levomethadyl acetate, methadone).

Quetiapine should also be avoided in circumstances that may increase the risk of occurrence of torsade de pointes and/or sudden death including (1) a history of cardiac arrhythmias such as bradycardia; (2) hypokalemia or hypomagnesemia; (3) concomitant use of other drugs that prolong the QTc interval; and (4) presence of congenital prolongation of the QT interval.

Caution should also be exercised when quetiapine is prescribed in patients with increased risk of QT prolongation (e.g., cardiovascular disease, family history of QT prolongation, the elderly, congestive heart failure, and heart hypertrophy).

5.13 Seizures

During clinical trials, seizures occurred in 0.5% (20/3490) of patients treated with SEROQUEL compared to 0.2% (2/954) on placebo and 0.7% (4/527) on active control drugs. As with other antipsychotics, SEROQUEL should be used cautiously in patients with a history of seizures or with conditions that potentially lower the seizure threshold, e.g., Alzheimer’s dementia. Conditions that lower the seizure threshold may be more prevalent in a population of 65 years or older.

5.14 Hypothyroidism

Adults: Clinical trials with quetiapine demonstrated dose-related decreases in thyroid hormone levels. The reduction in total and free thyroxine (T4) of approximately 20% at the higher end of the therapeutic dose range was maximal in the first six weeks of treatment and maintained without adaptation or progression during more chronic therapy. In nearly all cases, cessation of quetiapine treatment was associated with a reversal of the effects on total and free T4, irrespective of the duration of treatment. The mechanism by which quetiapine effects the thyroid axis is unclear. If there is an effect on the hypothalamic-pituitary axis, measurement of TSH alone may not accurately reflect a patient’s thyroid status. Therefore, both TSH and free T4, in addition to clinical assessment, should be measured at baseline and at follow-up.

In the mania adjunct studies, where SEROQUEL was added to lithium or divalproex, 12% (24/196) of SEROQUEL treated patients compared to 7% (15/203) of placebo-treated patients had elevated TSH levels. Of the SEROQUEL treated patients with elevated TSH levels, 3 had simultaneous low free T4 levels (free T4 <0.8 LLN).

About 0.7% (26/3489) of SEROQUEL patients did experience TSH increases in monotherapy studies. Some patients with TSH increases needed replacement thyroid treatment.

In all quetiapine trials, the incidence of shifts in thyroid hormones and TSH were1: decrease in free T4 (<0.8 LLN), 2.0% (357/17513); decrease in total T4 (<0.8LLN), 4.0% (75/1861); decrease in free T3 (<0.8 LLN), 0.4% (53/13766); decrease in total T3 (<0.8LLN), 2.0% (26/1312), and increase in TSH (>5mIU/L), 4.9% (956/19412). In eight patients, where TBG was measured, levels of TBG were unchanged.

Table 8 shows the incidence of these shifts in short-term placebo-controlled clinical trials.

Table 8: Incidence of Shifts in Thyroid Hormone Levels and TSH in Short-Term Placebo-Controlled Clinical Trials [Based on shifts from normal baseline to potentially clinically important value at any time post-baseline. Shifts in total T4, free T4, total T3, and free T3 are defined as <0.8 x LLN (pmol/L) and shift in TSH is >5 mlU/L at any time.] [Includes SEROQUEL and SEROQUEL XR data.]
Total T4 |  | Free T4 |  | Total T3 |  | Free T3 |  | TSH
Quetiapine | Placebo | Quetiapine | Placebo | Quetiapine | Placebo | Quetiapine | Placebo | Quetiapine | Placebo
3.4 %; (37/1097) | 0.6%; (4/651) | 0.7%; (52/7218) | 0.1%; (4/3668) | 0.5%; (2/369) | 0.0%; (0/113) | 0.2%; (11/5673) | 0.0%; (1/2679) | 3.2%; (240/7587) | 2.7%; (105/3912)

In short-term placebo-controlled monotherapy trials, the incidence of reciprocal, shifts in T3 and TSH was 0.0 % for both quetiapine (1/4800) and placebo (0/2190) and for T4 and TSH the shifts were 0.1% (7/6154) for quetiapine versus 0.0% (1/3007) for placebo.

Children and Adolescents:

In acute placebo-controlled trials in children and adolescent patients with schizophrenia (6-week duration) or bipolar mania (3-week duration), the incidence of shifts for thyroid function values at any time for SEROQUEL treated patients and placebo-treated patients for elevated TSH was 2.9% (8/280) vs. 0.7% (1/138), respectively, and for decreased total thyroxine was 2.8% (8/289) vs. 0% (0/145), respectively. Of the SEROQUEL treated patients with elevated TSH levels, 1 had simultaneous low free T4 level at end of treatment.

5.15 Hyperprolactinemia

Adults: During clinical trials with quetiapine, the incidence of shifts in prolactin levels to a clinically significant value occurred in 3.6% (158/4416) of patients treated with quetiapine compared to 2.6% (51/1968) on placebo.

Children and Adolescents:

In acute placebo-controlled trials in children and adolescent patients with bipolar mania (3-week duration) or schizophrenia (6-week duration), the incidence of shifts in prolactin levels to a value (>20 µg/L males; >26 µg/L females at any time) was 13.4% (18/134) for SEROQUEL compared to 4% (3/75) for placebo in males and 8.7% (9/104) for SEROQUEL compared to 0% (0/39) for placebo in females.

Like other drugs that antagonize dopamine D2 receptors, SEROQUEL elevates prolactin levels in some patients and the elevation may persist during chronic administration. Hyperprolactinemia, regardless of etiology, may suppress hypothalamic GnRH, resulting in reduced pituitary gonadotrophin secretion. This, in turn, may inhibit reproductive function by impairing gonadal steroidogenesis in both female and male patients. Galactorrhea, amenorrhea, gynecomastia, and impotence have been reported in patients receiving prolactin-elevating compounds. Long-standing hyperprolactinemia when associated with hypogonadism may lead to decreased bone density in both female and male subjects.

Tissue culture experiments indicate that approximately one-third of human breast cancers are prolactin dependent in vitro, a factor of potential importance if the prescription of these drugs is considered in a patient with previously detected breast cancer. As is common with compounds which increase prolactin release, mammary gland, and pancreatic islet cell neoplasia (mammary adenocarcinomas, pituitary, and pancreatic adenomas) was observed in carcinogenicity studies conducted in mice and rats [see Nonclinical Toxicology (13.1)]. Published epidemiologic studies have shown inconsistent results when exploring the potential association between hyperprolactinemia and breast cancer.

5.16 Potential for Cognitive and Motor Impairment

Somnolence was a commonly reported adverse event reported in patients treated with SEROQUEL especially during the 3-5 day period of initial dose-titration. In schizophrenia trials, somnolence was reported in 18% (89/510) of patients on SEROQUEL compared to 11% (22/206) of placebo patients. In acute bipolar mania trials using SEROQUEL as monotherapy, somnolence was reported in 16% (34/209) of patients on SEROQUEL compared to 4% of placebo patients. In acute bipolar mania trials using SEROQUEL as adjunct therapy, somnolence was reported in 34% (66/196) of patients on SEROQUEL compared to 9% (19/203) of placebo patients. In bipolar depression trials, somnolence was reported in 57% (398/698) of patients on SEROQUEL compared to 15% (51/347) of placebo patients. Since SEROQUEL has the potential to impair judgment, thinking, or motor skills, patients should be cautioned about performing activities requiring mental alertness, such as operating a motor vehicle (including automobiles) or operating hazardous machinery until they are reasonably certain that SEROQUEL therapy does not affect them adversely. Somnolence may lead to falls.

5.17 Body Temperature Regulation

Although not reported with SEROQUEL, disruption of the body's ability to reduce core body temperature has been attributed to antipsychotic agents. Appropriate care is advised when prescribing SEROQUEL for patients who will be experiencing conditions which may contribute to an elevation in core body temperature, e.g., exercising strenuously, exposure to extreme heat, receiving concomitant medication with anticholinergic activity, or being subject to dehydration.

5.18 Dysphagia

Esophageal dysmotility and aspiration have been associated with antipsychotic drug use. Aspiration pneumonia is a common cause of morbidity and mortality in elderly patients, in particular those with advanced Alzheimer's dementia. SEROQUEL and other antipsychotic drugs should be used cautiously in patients at risk for aspiration pneumonia.

5.19 Discontinuation Syndrome

Acute withdrawal symptoms, such as insomnia, nausea, and vomiting have been described after abrupt cessation of atypical antipsychotic drugs, including SEROQUEL. In short-term placebo-controlled, monotherapy clinical trials with SEROQUEL XR that included a discontinuation phase which evaluated discontinuation symptoms, the aggregated incidence of patients experiencing one or more discontinuation symptoms after abrupt cessation was 12.1% (241/1993) for SEROQUEL XR and 6.7% (71/1065) for placebo. The incidence of the individual adverse reactions (i.e., insomnia, nausea, headache, diarrhea, vomiting, dizziness, and irritability) did not exceed 5.3% in any treatment group and usually resolved after 1 week post-discontinuation. Gradual withdrawal is advised [see Use in Specific Populations (8.1)].

5.20 Anticholinergic (antimuscarinic) Effects

Norquetiapine, an active metabolite of quetiapine, has moderate to strong affinity for several muscarinic receptor subtypes. This contributes to anticholinergic adverse reactions when SEROQUEL is used at therapeutic doses, taken concomitantly with other anticholinergic medications, or taken in overdose. SEROQUEL should be used with caution in patients receiving medications having anticholinergic (antimuscarinic) effects [see Drug Interactions (7.1), Overdosage (10.1), and Clinical Pharmacology (12.1)].

Constipation was a commonly reported adverse event in patients treated with quetiapine and represents a risk factor for intestinal obstruction. Intestinal obstruction has been reported with quetiapine, including fatal reports in patients who were receiving multiple concomitant medications that decrease intestinal motility.

SEROQUEL should be used with caution in patients with a current diagnosis or prior history of urinary retention, clinically significant prostatic hypertrophy, or constipation.

6 ADVERSE REACTIONS

The following adverse reactions are discussed in more detail in other sections of the labeling:

- Increased mortality in elderly patients with dementia-related psychosis [see Warnings and Precautions (5.1)]
- Suicidal thoughts and behaviors in adolescents and young adults [see Warnings and Precautions (5.2)]
- Cerebrovascular adverse reactions, including stroke in elderly patients with dementia-related psychosis [see Warnings and Precautions (5.3)]
- Neuroleptic Malignant Syndrome (NMS) [see Warnings and Precautions (5.4)]
- Metabolic changes (hyperglycemia, dyslipidemia, weight gain) [see Warnings and Precautions (5.5)]
- Tardive dyskinesia [see Warnings and Precautions (5.6)]
- Hypotension [see Warnings and Precautions (5.7)]
- Falls [see Warnings and Precautions (5.8)]
- Increases in blood pressure (children and adolescents) [see Warnings and Precautions (5.9)]
- Leukopenia, neutropenia and agranulocytosis [see Warnings and Precautions (5.10)]
- Cataracts [see Warnings and Precautions (5.11)]
- QT Prolongation [see Warnings and Precautions (5.12)]
- Seizures [see Warnings and Precautions (5.13)]
- Hypothyroidism [see Warnings and Precautions (5.14)]
- Hyperprolactinemia [see Warnings and Precautions (5.15)]
- Potential for cognitive and motor impairment [see Warnings and Precautions (5.16)]
- Body temperature regulation [see Warnings and Precautions (5.17)]
- Dysphagia [see Warnings and Precautions (5.18)]
- Discontinuation Syndrome [see Warnings and Precautions (5.19)]
- Anticholinergic (antimuscarinic) Effects [see Warnings and Precautions (5.20)]

6.1 Clinical Study Experience

Because clinical studies are conducted under widely varying conditions, adverse reaction rates observed in the clinical studies of a drug cannot be directly compared to rates in the clinical studies of another drug and may not reflect the rates observed in practice.

Adults:

The information below is derived from a clinical trial database for SEROQUEL consisting of over 4300 patients. This database includes 698 patients exposed to SEROQUEL for the treatment of bipolar depression, 405 patients exposed to SEROQUEL for the treatment of acute bipolar mania (monotherapy and adjunct therapy), 646 patients exposed to SEROQUEL for the maintenance treatment of bipolar I disorder as adjunct therapy, and approximately 2600 patients and/or normal subjects exposed to 1 or more doses of SEROQUEL for the treatment of schizophrenia.

Of these approximately 4,300 subjects, approximately 4000 (2300 in schizophrenia, 405 in acute bipolar mania, 698 in bipolar depression, and 646 for the maintenance treatment of bipolar I disorder) were patients who participated in multiple dose effectiveness trials, and their experience corresponded to approximately 2400 patient-years. The conditions and duration of treatment with SEROQUEL varied greatly and included (in overlapping categories) open-label and double-blind phases of studies, inpatients and outpatients, fixed-dose and dose-titration studies, and short-term or longer-term exposure. Adverse reactions were assessed by collecting adverse reactions, results of physical examinations, vital signs, weights, laboratory analyses, ECGs, and results of ophthalmologic examinations.

The stated frequencies of adverse reactions represent the proportion of individuals who experienced, at least once, an adverse reaction of the type listed.

Adverse Reactions Associated with Discontinuation of Treatment in Short-Term, Placebo-Controlled Trials

Schizophrenia: Overall, there was little difference in the incidence of discontinuation due to adverse reactions (4% for SEROQUEL vs. 3% for placebo) in a pool of controlled trials. However, discontinuations due to somnolence (0.8% SEROQUEL vs. 0% placebo) and hypotension (0.4% SEROQUEL vs. 0% placebo) were considered to be drug related [see Warnings and Precautions (5.7 and 5.19)].

Bipolar Disorder:

Mania: Overall, discontinuations due to adverse reactions were 5.7% for SEROQUEL vs. 5.1% for placebo in monotherapy and 3.6% for SEROQUEL vs. 5.9% for placebo in adjunct therapy.

Depression: Overall, discontinuations due to adverse reactions were 12.3% for SEROQUEL 300 mg vs. 19.0% for SEROQUEL 600 mg and 5.2% for placebo.

Commonly Observed Adverse Reactions in Short-Term, Placebo-Controlled Trials:

In the acute therapy of schizophrenia (up to 6 weeks) and bipolar mania (up to 12 weeks) trials, the most commonly observed adverse reactions associated with the use of SEROQUEL monotherapy (incidence of 5% or greater) and observed at a rate on SEROQUEL at least twice that of placebo were somnolence (18%), dizziness (11%), dry mouth (9%), constipation (8%), ALT increased (5%), weight gain (5%), and dyspepsia (5%).

Adverse Reactions Occurring at an Incidence of 2% or More Among SEROQUEL Treated Patients in Short-Term, Placebo-Controlled Trials:

The prescriber should be aware that the figures in the tables and tabulations cannot be used to predict the incidence of side effects in the course of usual medical practice where patient characteristics and other factors differ from those that prevailed in the clinical trials. Similarly, the cited frequencies cannot be compared with figures obtained from other clinical investigations involving different treatments, uses, and investigators. The cited figures, however, do provide the prescribing physician with some basis for estimating the relative contribution of drug and non-drug factors to the side effect incidence in the population studied.

Table 9 enumerates the incidence, rounded to the nearest percent, of adverse reactions that occurred during acute therapy of schizophrenia (up to 6 weeks) and bipolar mania (up to 12 weeks) in 2% or more of patients treated with SEROQUEL (doses ranging from 75 to 800 mg/day) where the incidence in patients treated with SEROQUEL was greater than the incidence in placebo-treated patients.

Table 9: Adverse Reaction Incidence in 3- to 12-Week Placebo-Controlled Clinical Trials for the Treatment of Schizophrenia and Bipolar Mania (Monotherapy)
Preferred Term | SEROQUEL (n=719) | PLACEBO (n=404)
Headache | 21% | 14%
Agitation | 20% | 17%
Somnolence | 18% | 8%
Dizziness | 11% | 5%
Dry Mouth | 9% | 3%
Constipation | 8% | 3%
Pain | 7% | 5%
Tachycardia | 6% | 4%
Vomiting | 6% | 5%
Asthenia | 5% | 3%
Dyspepsia | 5% | 1%
Weight Gain | 5% | 1%
ALT Increased | 5% | 1%
Anxiety | 4% | 3%
Pharyngitis | 4% | 3%
Rash | 4% | 2%
Abdominal Pain | 4% | 1%
Postural Hypotension | 4% | 1%
Back Pain | 3% | 1%
AST Increased | 3% | 1%
Rhinitis | 3% | 1%
Fever | 2% | 1%
Gastroenteritis | 2% | 0%
Amblyopia | 2% | 1%

In the acute adjunct therapy of bipolar mania (up to 3 weeks) studies, the most commonly observed adverse reactions associated with the use of SEROQUEL (incidence of 5% or greater) and observed at a rate on SEROQUEL at least twice that of placebo were somnolence (34%), dry mouth (19%), asthenia (10%), constipation (10%), abdominal pain (7%), postural hypotension (7%), pharyngitis (6%), and weight gain (6%).

Table 10 enumerates the incidence, rounded to the nearest percent, of adverse reactions that occurred during therapy (up to 3 weeks) of acute mania in 2% or more of patients treated with SEROQUEL (doses ranging from 100 to 800 mg/day) used as adjunct therapy to lithium and divalproex where the incidence in patients treated with SEROQUEL was greater than the incidence in placebo-treated patients.

Table 10: Adverse Reaction Incidence in 3-Week Placebo-Controlled Clinical Trials for the Treatment of Bipolar Mania (Adjunct Therapy)
Preferred Term | SEROQUEL; (n=196) | PLACEBO; (n=203)
Somnolence | 34% | 9%
Dry Mouth | 19% | 3%
Headache | 17% | 13%
Asthenia | 10% | 4%
Constipation | 10% | 5%
Dizziness | 9% | 6%
Tremor | 8% | 7%
Abdominal Pain | 7% | 3%
Postural Hypotension | 7% | 2%
Agitation | 6% | 4%
Weight Gain | 6% | 3%
Pharyngitis | 6% | 3%
Back Pain | 5% | 3%
Hypertonia | 4% | 3%
Rhinitis | 4% | 2%
Peripheral Edema | 4% | 2%
Twitching | 4% | 1%
Dyspepsia | 4% | 3%
Depression | 3% | 2%
Amblyopia | 3% | 2%
Speech Disorder | 3% | 1%
Hypotension | 3% | 1%
Hormone Level Altered | 3% | 0%
Heaviness | 2% | 1%
Infection | 2% | 1%
Fever | 2% | 1%
Hypertension | 2% | 1%
Tachycardia | 2% | 1%
Increased Appetite | 2% | 1%
Hypothyroidism | 2% | 1%
Incoordination | 2% | 1%
Thinking Abnormal | 2% | 0%
Anxiety | 2% | 0%
Ataxia | 2% | 0%
Sinusitis | 2% | 1%
Sweating | 2% | 1%
Urinary Tract Infection | 2% | 1%

In bipolar depression studies (up to 8 weeks), the most commonly observed adverse reactions associated with the use of SEROQUEL (incidence of 5% or greater) and observed at a rate on SEROQUEL at least twice that of placebo were somnolence (57%), dry mouth (44%), dizziness (18%), constipation (10%), and lethargy (5%).

Table 11 enumerates the incidence, rounded to the nearest percent, of adverse reactions that occurred during therapy (up to 8 weeks) of bipolar depression in 2% or more of patients treated with SEROQUEL (doses of 300 and 600 mg/day) where the incidence in patients treated with SEROQUEL was greater than the incidence in placebo-treated patients.

Table 11: Adverse Reaction Incidence in 8-Week Placebo-Controlled Clinical Trials for the Treatment of Bipolar Depression
Preferred Term | SEROQUEL; (n=698) | PLACEBO; (n=347)
Somnolence [Somnolence combines adverse reaction terms somnolence and sedation] | 57% | 15%
Dry Mouth | 44% | 13%
Dizziness | 18% | 7%
Constipation | 10% | 4%
Fatigue | 10% | 8%
Dyspepsia | 7% | 4%
Vomiting | 5% | 4%
Increased Appetite | 5% | 3%
Lethargy | 5% | 2%
Nasal Congestion | 5% | 3%
Orthostatic Hypotension | 4% | 3%
Akathisia | 4% | 1%
Palpitations | 4% | 1%
Vision Blurred | 4% | 2%
Weight increased | 4% | 1%
Arthralgia | 3% | 2%
Paraesthesia | 3% | 2%
Cough | 3% | 1%
Extrapyramidal Disorder | 3% | 1%
Irritability | 3% | 1%
Dysarthria | 3% | 0%
Hypersomnia | 3% | 0%
Sinus Congestion | 2% | 1%
Abnormal Dreams | 2% | 1%
Tremor | 2% | 1%
Gastroesophageal Reflux Disease | 2% | 1%
Pain in Extremity | 2% | 1%
Asthenia | 2% | 1%
Balance Disorder | 2% | 1%
Hypoesthesia | 2% | 1%
Dysphagia | 2% | 0%
Restless Legs Syndrome | 2% | 0%

Explorations for interactions on the basis of gender, age, and race did not reveal any clinically meaningful differences in the adverse reaction occurrence on the basis of these demographic factors.

Dose Dependency of Adverse Reactions in Short-Term, Placebo-Controlled Trials

Dose-related Adverse Reactions: Spontaneously elicited adverse reaction data from a study of schizophrenia comparing five fixed doses of SEROQUEL (75 mg, 150 mg, 300 mg, 600 mg, and 750 mg/day) to placebo were explored for dose-relatedness of adverse reactions. Logistic regression analyses revealed a positive dose response (p<0.05) for the following adverse reactions: dyspepsia, abdominal pain, and weight gain.

Adverse Reactions in clinical trials with quetiapine and not listed elsewhere in the label:

The following adverse reactions have also been reported with quetiapine: nightmares, hypersensitivity, and elevations in serum creatine phosphokinase (not associated with NMS), galactorrhea, bradycardia (which may occur at or near initiation of treatment and be associated with hypotension and/or syncope) decreased platelets, somnambulism (and other related events), elevations in gamma-GT levels, hypothermia, dyspnea, eosinophilia, urinary retention, intestinal obstruction and priapism.

Extrapyramidal Symptoms (EPS):

Dystonia

Class Effect: Symptoms of dystonia, prolonged abnormal contractions of muscle groups, may occur in susceptible individuals during the first few days of treatment. Dystonic symptoms include: spasm of the neck muscles, sometimes progressing to tightness of the throat, swallowing difficulty, difficulty breathing, and/or protrusion of the tongue. While these symptoms can occur at low doses, they occur more frequently and with greater severity with high potency and at higher doses of first generation antipsychotic drugs. An elevated risk of acute dystonia is observed in males and younger age groups.

Four methods were used to measure EPS: (1) Simpson-Angus total score (mean change from baseline) which evaluates Parkinsonism and akathisia, (2) Barnes Akathisia Rating Scale (BARS) Global Assessment Score, (3) incidence of spontaneous complaints of EPS (akathisia, akinesia, cogwheel rigidity, extrapyramidal syndrome, hypertonia, hypokinesia, neck rigidity, and tremor), and (4) use of anticholinergic medications to treat EPS.

Adults: Data from one 6-week clinical trial of schizophrenia comparing five fixed doses of SEROQUEL (75, 150, 300, 600, 750 mg/day) provided evidence for the lack of extrapyramidal symptoms (EPS) and dose-relatedness for EPS associated with SEROQUEL treatment. Three methods were used to measure EPS: (1) Simpson-Angus total score (mean change from baseline) which evaluates Parkinsonism and akathisia, (2) incidence of spontaneous complaints of EPS (akathisia, akinesia, cogwheel rigidity, extrapyramidal syndrome, hypertonia, hypokinesia, neck rigidity, and tremor), and (3) use of anticholinergic medications to EPS.

In Table 12, dystonic event included nuchal rigidity, hypertonia, dystonia, muscle rigidity, oculogyration; parkinsonism included cogwheel rigidity, tremor, drooling, hypokinesia; akathisia included akathisia, psychomotor agitation; dyskinetic event included tardive dyskinesia, dyskinesia, choreoathetosis; and other extrapyramidal event included restlessness, extrapyramidal disorder, movement disorder.

Table 12: Adverse Reactions Associated with EPS in a Short-Term, Placebo-Controlled Multiple Fixed-Dose Phase III Schizophrenia Trial (6 weeks duration)
Preferred Term | SEROQUEL; 75 mg/day; (N=53) |  | SEROQUEL; 150 mg/day; (N=48) |  | SEROQUEL; 300 mg/day; (N=52) |  | SEROQUEL; 600 mg/day; (N=51) |  | SEROQUEL; 750 mg/day; (N=54) |  | Placebo; (N=51)
 | n | % | n | % | n | % | n | % | n | % | n | %
Dystonic event | 2 | 3.8 | 2 | 4.2 | 0 | 0.0 | 2 | 3.9 | 3 | 5.6 | 4 | 7.8
Parkinsonism | 2 | 3.8 | 0 | 0.0 | 1 | 1.9 | 1 | 2.0 | 1 | 1.9 | 4 | 7.8
Akathisia | 1 | 1.9 | 1 | 2.1 | 0 | 0.0 | 0 | 0.0 | 1 | 1.9 | 4 | 7.8
Dyskinetic event | 2 | 3.8 | 0 | 0.0 | 0 | 0.0 | 1 | 2.0 | 0 | 0.0 | 0 | 0.0
Other extrapyramidal event | 2 | 3.8 | 0 | 0.0 | 3 | 5.8 | 3 | 5.9 | 1 | 1.9 | 4 | 7.8

Parkinsonism incidence rates as measured by the Simpson-Angus total score for placebo and the five fixed doses (75, 150, 300, 600, 750 mg/day) were: -0.6; -1.0, -1.2; -1.6; -1.8, and -1.8. The rate of anticholinergic medication use to treat EPS for placebo and the five fixed doses was: 14%; 11%; 10%; 8%; 12%, and 11%.

In six additional placebo-controlled clinical trials (3 in acute mania and 3 in schizophrenia) using variable doses of SEROQUEL, there were no differences between the SEROQUEL and placebo treatment groups in the incidence of EPS, as assessed by Simpson-Angus total scores, spontaneous complaints of EPS and the use of concomitant anticholinergic medications to treat EPS.

In two placebo-controlled clinical trials for the treatment of bipolar depression using 300 mg and 600 mg of SEROQUEL, the incidence of adverse reactions potentially related to EPS was 12% in both dose groups and 6% in the placebo group. In these studies, the incidence of the individual adverse reactions (akathisia, extrapyramidal disorder, tremor, dyskinesia, dystonia, restlessness, muscle contractions involuntary, psychomotor hyperactivity, and muscle rigidity) were generally low and did not exceed 4% in any treatment group.

The 3 treatment groups were similar in mean change in SAS total score and BARS Global Assessment score at the end of treatment. The use of concomitant anticholinergic medications was infrequent and similar across the three treatment groups.

Children and Adolescents

The information below is derived from a clinical trial database for SEROQUEL consisting of over 1000 pediatric patients. This database includes 677 patients exposed to SEROQUEL for the treatment of schizophrenia and 393 children and adolescents (10-17 years old) exposed to SEROQUEL for the treatment of acute bipolar mania.

Adverse Reactions Associated with Discontinuation of Treatment in Short-Term, Placebo-Controlled Trials

Schizophrenia: The incidence of discontinuation due to adverse reactions for quetiapine-treated and placebo-treated patients was 8.2% and 2.7%, respectively. The adverse event leading to discontinuation in 1% or more of patients on SEROQUEL and at a greater incidence than placebo was somnolence (2.7% and 0% for placebo).

Bipolar I Mania: The incidence of discontinuation due to adverse reactions for quetiapine-treated and placebo-treated patients was 11.4% and 4.4%, respectively. The adverse reactions leading to discontinuation in 2% or more of patients on SEROQUEL and at a greater incidence than placebo were somnolence (4.1% vs. 1.1%) and fatigue (2.1% vs. 0).

Commonly Observed Adverse Reactions in Short-Term, Placebo-Controlled Trials

In therapy for schizophrenia (up to 6 weeks), the most commonly observed adverse reactions associated with the use of quetiapine in adolescents (incidence of 5% or greater and quetiapine incidence at least twice that for placebo) were somnolence (34%), dizziness (12%), dry mouth (7%), tachycardia (7%).

In bipolar mania therapy (up to 3 weeks) the most commonly observed adverse reactions associated with the use of quetiapine in children and adolescents (incidence of 5% or greater and quetiapine incidence at least twice that for placebo) were somnolence (53%), dizziness (18%), fatigue (11%), increased appetite (9%), nausea (8%), vomiting (8%), tachycardia (7%), dry mouth (7%), and weight increased (6%).

In an acute (8-week) SEROQUEL XR trial in children and adolescents (10-17 years of age) with bipolar depression, in which efficacy was not established, the most commonly observed adverse reactions associated with the use of SEROQUEL XR (incidence of 5% or greater and at least twice that for placebo) were dizziness 7%, diarrhea 5%, fatigue 5%, and nausea 5%.

Adverse Reactions Occurring at an Incidence of ≥ 2% among SEROQUEL Treated Patients in Short-Term, Placebo-Controlled Trials

Schizophrenia (Adolescents, 13-17 years old)

The following findings were based on a 6-week placebo-controlled trial in which quetiapine was administered in either doses of 400 or 800 mg/day.

Table 13 enumerates the incidence, rounded to the nearest percent, of adverse reactions that occurred during therapy (up to 6 weeks) of schizophrenia in 2% or more of patients treated with SEROQUEL (doses of 400 or 800 mg/day) where the incidence in patients treated with SEROQUEL was at least twice the incidence in placebo-treated patients.

Adverse reactions that were potentially dose-related with higher frequency in the 800 mg group compared to the 400 mg group included dizziness (8% vs. 15%), dry mouth (4% vs. 10%), and tachycardia (6% vs. 11%).

Table 13: Adverse Reaction Incidence in a 6-Week Placebo-Controlled Clinical Trial for the Treatment of Schizophrenia in Adolescent Patients
Preferred Term | SEROQUEL 400 mg; (n=73) | SEROQUEL 800 mg; (n=74) | Placebo; (n=75)
Somnolence [Somnolence combines adverse reaction terms somnolence and sedation.] | 33% | 35% | 11%
Dizziness | 8% | 15% | 5%
Dry Mouth | 4% | 10% | 1%
Tachycardia [Tachycardia combines adverse reaction terms tachycardia and sinus tachycardia.] | 6% | 11% | 0%
Irritability | 3% | 5% | 0%
Arthralgia | 1% | 3% | 0%
Asthenia | 1% | 3% | 1%
Back Pain | 1% | 3% | 0%
Dyspnea | 0% | 3% | 0%
Abdominal Pain | 3% | 1% | 0%
Anorexia | 3% | 1% | 0%
Tooth Abscess | 3% | 1% | 0%
Dyskinesia | 3% | 0% | 0%
Epistaxis | 3% | 0% | 1%
Muscle Rigidity | 3% | 0% | 0%

Bipolar I Mania (Children and Adolescents 10-17 years old)

The following findings were based on a 3-week placebo-controlled trial in which quetiapine was administered in either doses of 400 or 600 mg/day.

Commonly Observed Adverse Reactions

In bipolar mania therapy (up to 3 weeks) the most commonly observed adverse reactions associated with the use of quetiapine in children and adolescents (incidence of 5% or greater and quetiapine incidence at least twice that for placebo) were somnolence (53%), dizziness (18%), fatigue (11%), increased appetite (9%), nausea (8%), vomiting (8%), tachycardia (7%), dry mouth (7%), and weight increased (6%).

Table 14 enumerates the incidence, rounded to the nearest percent, of adverse reactions that occurred during therapy (up to 3 weeks) of bipolar mania in 2% or more of patients treated with SEROQUEL (doses of 400 or 600 mg/day) where the incidence in patients treated with SEROQUEL was greater than the incidence in placebo-treated patients.

Adverse reactions that were potentially dose-related with higher frequency in the 600 mg group compared to the 400 mg group included somnolence (50% vs. 57%), nausea (6% vs. 10%), and tachycardia (6% vs. 9%).

Table 14: Adverse Reactions in a 3-Week Placebo-Controlled Clinical Trial for the Treatment of Bipolar Mania in Children and Adolescent Patients
Preferred Term | SEROQUEL; 400 mg; (n=95) | SEROQUEL; 600 mg; (n=98) | Placebo; (n=90)
Somnolence [Somnolence combines adverse reactions terms somnolence and sedation.] | 50% | 57% | 14%
Dizziness | 19% | 17% | 2%
Nausea | 6% | 10% | 4%
Fatigue | 14% | 9% | 4%
Increased Appetite | 10% | 9% | 1%
Tachycardia [Tachycardia combines adverse reaction terms tachycardia and sinus tachycardia.] | 6% | 9% | 1%
Dry Mouth | 7% | 7% | 0%
Vomiting | 8% | 7% | 3%
Nasal Congestion | 3% | 6% | 2%
Weight Increased | 6% | 6% | 0%
Irritability | 3% | 5% | 1%
Pyrexia | 1% | 4% | 1%
Aggression | 1% | 3% | 0%
Musculoskeletal Stiffness | 1% | 3% | 1%
Accidental Overdose | 0% | 2% | 0%
Acne | 3% | 2% | 0%
Arthralgia | 4% | 2% | 1%
Lethargy | 2% | 2% | 0%
Pallor | 1% | 2% | 0%
Stomach Discomfort | 4% | 2% | 1%
Syncope | 2% | 2% | 0%
Vision Blurred | 3% | 2% | 0%
Constipation | 4% | 2% | 0%
Ear Pain | 2% | 0% | 0%
Paresthesia | 2% | 0% | 0%
Sinus Congestion | 3% | 0% | 0%
Thirst | 2% | 0% | 0%

Extrapyramidal Symptoms:

In a short-term placebo-controlled monotherapy trial in adolescent patients with schizophrenia (6-week duration), the aggregated incidence of extrapyramidal symptoms was 12.9% (19/147) for SEROQUEL and 5.3% (4/75) for placebo, though the incidence of the individual adverse reactions (akathisia, tremor, extrapyramidal disorder, hypokinesia, restlessness, psychomotor hyperactivity, muscle rigidity, dyskinesia) did not exceed 4.1% in any treatment group. In a short-term placebo-controlled monotherapy trial in children and adolescent patients with bipolar mania (3-week duration), the aggregated incidence of extrapyramidal symptoms was 3.6% (7/193) or SEROQUEL and 1.1% (1/90) for placebo.

Table 15 presents a listing of patients with adverse reactions potentially associated with extrapyramidal symptoms in the short-term placebo-controlled monotherapy trial in adolescent patients with schizophrenia (6-week duration).

In Tables 15-16, dystonic event included nuchal rigidity, hypertonia, and muscle rigidity; parkinsonism included cogwheel rigidity and tremor; akathisia included akathisia only; dyskinetic event included tardive dyskinesia, dyskinesia, and choreoathetosis; and other extrapyramidal event included restlessness and extrapyramidal disorder.

Table 15: Adverse Reactions Associated with Extrapyramidal Symptoms in the Placebo-Controlled Trial in Adolescent Patients with Schizophrenia (6-week duration)
Preferred Term | SEROQUEL; 400 mg/day; (N=73) |  | SEROQUEL; 800 mg/day; (N=74) |  | All; SEROQUEL; (N=147) |  | Placebo; (N=75)
 | n | % | n | % | n | % | n | %
Dystonic event | 2 | 2.7 | 0 | 0.0 | 2 | 1.4 | 0 | 0.0
Parkinsonism | 4 | 5.5 | 4 | 5.4 | 8 | 5.4 | 2 | 2.7
Akathisia | 3 | 4.1 | 4 | 5.4 | 7 | 4.8 | 3 | 4.0
Dyskinetic event | 2 | 2.7 | 0 | 0.0 | 2 | 1.4 | 0 | 0.0
Other Extrapyramidal Event | 2 | 2.7 | 2 | 2.7 | 4 | 2.7 | 0 | 0.0

Table 16 presents a listing of patients with adverse reactions associated with extrapyramidal symptoms in a short-term placebo-controlled monotherapy trial in children and adolescent patients with bipolar mania (3-week duration).

Table 16: Adverse Reactions Associated with Extrapyramidal Symptoms in a Placebo-Controlled Trial in Children and Adolescent Patients with Bipolar I Mania (3-week duration)
Preferred Term [There were no adverse reactions with the preferred term of dystonic or dyskinetic events.] | SEROQUEL; 400 mg/day; (N=95) |  | SEROQUEL; 600 mg/day; (N=98) |  | All SEROQUEL; (N=193) |  | Placebo; (N=90)
 | n | % | n | % | n | % | n | %
Parkinsonism | 2 | 2.1 | 1 | 1.0 | 3 | 1.6 | 1 | 1.1
Akathisia | 1 | 1.0 | 1 | 1.0 | 2 | 1.0 | 0 | 0.0
Other; Extrapyramidal; Event | 1 | 1.1 | 1 | 1.0 | 2 | 1.0 | 0 | 0.0

Laboratory, ECG, and vital sign changes observed in clinical studies

Laboratory Changes:

Neutrophil Counts

Adults: In placebo-controlled monotherapy clinical trials involving 3368 patients on quetiapine and 1515 on placebo, the incidence of at least one occurrence of neutrophil count <1.0 x 10^9/L among patients with a normal baseline neutrophil count and at least one available follow up laboratory measurement was 0.3% (10/2967) in patients treated with quetiapine, compared to 0.1% (2/1349) in patients treated with placebo [see Warnings and Precautions (5.10)].

Transaminase Elevations

Adults: Asymptomatic, transient, and reversible elevations in serum transaminases (primarily ALT) have been reported. In schizophrenia trials in adults, the proportions of patients with transaminase elevations of >3 times the upper limits of the normal reference range in a pool of 3- to 6-week placebo-controlled trials were approximately 6% (29/483) for SEROQUEL compared to 1% (3/194) for placebo. In acute bipolar mania trials in adults, the proportions of patients with transaminase elevations of >3 times the upper limits of the normal reference range in a pool of 3- to 12-week placebo-controlled trials were approximately 1% for both SEROQUEL (3/560) and placebo (3/294). These hepatic enzyme elevations usually occurred within the first 3 weeks of drug treatment and promptly returned to pre-study levels with ongoing treatment with SEROQUEL. In bipolar depression trials, the proportions of patients with transaminase elevations of >3 times the upper limits of the normal reference range in two 8-week placebo-controlled trials was 1% (5/698) for SEROQUEL and 2% (6/347) for placebo.

Decreased Hemoglobin

Adults: In short-term placebo-controlled trials, decreases in hemoglobin to ≤13 g/dL males, ≤12 g/dL females on at least one occasion occurred in 8.3% (594/7155) of quetiapine-treated patients compared to 6.2% (219/3536) of patients treated with placebo. In a database of controlled and uncontrolled clinical trials, decreases in hemoglobin to ≤13 g/dL males, ≤12 g/dL females on at least one occasion occurred in 11% (2277/20729) of quetiapine-treated patients.

Interference with Urine Drug Screens

There have been literature reports suggesting false positive results in urine enzyme immunoassays for methadone and tricyclic antidepressants in patients who have taken quetiapine. Caution should be exercised in the interpretation of positive urine drug screen results for these drugs, and confirmation by alternative analytical technique (e.g., chromatographic methods) should be considered.

ECG Changes

Adults: Between-group comparisons for pooled placebo-controlled trials revealed no statistically significant SEROQUEL/placebo differences in the proportions of patients experiencing potentially important changes in ECG parameters, including QT, QTc, and PR intervals. However, the proportions of patients meeting the criteria for tachycardia were compared in four 3- to 6-week placebo-controlled clinical trials for the treatment of schizophrenia revealing a 1% (4/399) incidence for SEROQUEL compared to 0.6% (1/156) incidence for placebo. In acute (monotherapy) bipolar mania trials the proportions of patients meeting the criteria for tachycardia was 0.5% (1/192) for SEROQUEL compared to 0% (0/178) incidence for placebo. In acute bipolar mania (adjunct) trials the proportions of patients meeting the same criteria was 0.6% (1/166) for SEROQUEL compared to 0% (0/171) incidence for placebo. In bipolar depression trials, no patients had heart rate increases to >120 beats per minute. SEROQUEL use was associated with a mean increase in heart rate, assessed by ECG, of 7 beats per minute compared to a mean increase of 1 beat per minute among placebo patients. This slight tendency to tachycardia in adults may be related to SEROQUEL's potential for inducing orthostatic changes [see Warnings and Precautions (5.7)].

Children and Adolescents: In the acute (6-week) schizophrenia trial in adolescents, increases in heart rate (>110 bpm) occurred in 5.2% (3/73) of patients receiving SEROQUEL 400 mg and 8.5% (5/74) of patients receiving SEROQUEL 800 mg compared to 0% (0/75) of patients receiving placebo. Mean increases in heart rate were 3.8 bpm and 11.2 bpm for SEROQUEL 400 mg and 800 mg groups, respectively, compared to a decrease of 3.3 bpm in the placebo group [see Warnings and Precautions (5.7)].

In the acute (3-week) bipolar mania trial in children and adolescents, increases in heart rate (>110 bpm) occurred in 1.1% (1/89) of patients receiving SEROQUEL 400 mg and 4.7% (4/85) of patients receiving SEROQUEL 600 mg compared to 0% (0/98) of patients receiving placebo. Mean increases in heart rate were 12.8 bpm and 13.4 bpm for SEROQUEL 400 mg and 600 mg groups, respectively, compared to a decrease of 1.7 bpm in the placebo group [see Warnings and Precautions (5.7)].

In an acute (8-week) SEROQUEL XR trial in children and adolescents (10-17 years of age) with bipolar depression, in which efficacy was not established, increases in heart rate (>110 bpm 10-12 years and 13-17 years) occurred in 0% of patients receiving SEROQUEL XR and 1.2% of patients receiving placebo. Mean increases in heart rate were 3.4 bpm for SEROQUEL XR, compared to 0.3 bpm in the placebo group [see Warnings and Precautions (5.7)].

6.2 Postmarketing Experience

The following adverse reactions were identified during post approval of SEROQUEL. Because these reactions are reported voluntarily from a population of uncertain size, it is not always possible to reliably estimate their frequency or establish a causal relationship to drug exposure.

Adverse reactions reported since market introduction which were temporally related to quetiapine therapy include anaphylactic reaction, cardiomyopathy, drug reaction with eosinophilia and systemic symptoms (DRESS), hyponatremia, myocarditis, nocturnal enuresis, pancreatitis, retrograde amnesia, rhabdomyolysis, syndrome of inappropriate antidiuretic hormone secretion (SIADH), Stevens-Johnson syndrome (SJS), toxic epidermal necrolysis (TEN), decreased platelet count, serious liver reactions (including hepatitis, liver necrosis, and hepatic failure), agranulocytosis, intestinal obstruction, ileus, colon ischemia, urinary retention, sleep apnea, acute generalized exanthematous pustulosis (AGEP), confusional state and cutaneous vasculitis, and fecal incontinence.

7 DRUG INTERACTIONS

7.1 Effect of Other Drugs on Quetiapine

The risks of using SEROQUEL in combination with other drugs have not been extensively evaluated in systematic studies. Given the primary CNS effects of SEROQUEL, caution should be used when it is taken in combination with other centrally acting drugs. SEROQUEL potentiated the cognitive and motor effects of alcohol in a clinical trial in subjects with selected psychotic disorders, and alcoholic beverages should be limited while taking quetiapine.

Quetiapine exposure is increased by the prototype CYP3A4 inhibitors (e.g., ketoconazole, itraconazole, indinavir, ritonavir, nefazodone, etc.) and decreased by the prototype CYP3A4 inducers (e.g., phenytoin, carbamazepine, rifampin, avasimibe, St. John’s wort etc.). Dose adjustment of quetiapine will be necessary if it is co-administered with potent CYP3A4 inducers or inhibitors.

CYP3A4 inhibitors:

Coadministration of ketoconazole, a potent inhibitor of cytochrome CYP3A4, resulted in significant increase in quetiapine exposure. The dose of SEROQUEL should be reduced to one sixth of the original dose if co-administered with a strong CYP3A4 inhibitor [see Dosage and Administration (2.5) and Clinical Pharmacology (12.3)].

CYP3A4 inducers:

Coadministration of quetiapine and phenytoin, a CYP3A4 inducer increased the mean oral clearance of quetiapine by 5-fold. Increased doses of SEROQUEL up to 5 fold may be required to maintain control of symptoms of schizophrenia in patients receiving quetiapine and phenytoin, or other known potent CYP3A4 inducers [see Dosage and Administration (2.6) and Clinical Pharmacology (12.3)]. When the CYP3A4 inducer is discontinued, the dose of SEROQUEL should be reduced to the original level within 7-14 days [see Dosage and Administration (2.6)].

Anticholinergic Drugs:

Concomitant treatment with quetiapine and other drugs with anticholinergic activity can increase the risk for severe gastrointestinal adverse reactions related to hypomotility. SEROQUEL should be used with caution in patients receiving medications having anticholinergic (antimuscarinic) effects [see Warnings and Precautions (5.20)].

The potential effects of several concomitant medications on quetiapine pharmacokinetics were studied [see Clinical Pharmacology (12.3)].

7.2 Effect of Quetiapine on Other Drugs

Because of its potential for inducing hypotension, SEROQUEL may enhance the effects of certain antihypertensive agents.

SEROQUEL may antagonize the effects of levodopa and dopamine agonists.

There are no clinically relevant pharmacokinetic interactions of Seroquel on other drugs based on the CYP pathway. Seroquel and its metabolites are non-inhibitors of major metabolizing CYP’s (1A2, 2C9, 2C19, 2D6, and 3A4).

8 USE IN SPECIFIC POPULATIONS

8.1 Pregnancy

Pregnancy Exposure Registry

There is a pregnancy exposure registry that monitors pregnancy outcomes in women exposed to atypical antipsychotics, including SEROQUEL, during pregnancy. Healthcare providers are encouraged to register patients by contacting the National Pregnancy Registry for Atypical Antipsychotics at 1-866-961-2388 or online at http://womensmentalhealth.org/clinical-and-research-programs/pregnancyregistry/

Risk Summary

Neonates exposed to antipsychotic drugs (including SEROQUEL) during the third trimester are at risk for extrapyramidal and/or withdrawal symptoms following delivery (see Clinical Considerations). Overall available data from published epidemiologic studies of pregnant women exposed to quetiapine have not established a drug-associated risk of major birth defects, miscarriage, or adverse maternal or fetal outcomes (see Data). There are risks to the mother associated with untreated schizophrenia, bipolar I, or major depressive disorder, and with exposure to antipsychotics, including SEROQUEL, during pregnancy (see Clinical Considerations).

In animal studies, embryo-fetal toxicity occurred including delays in skeletal ossification at approximately 1 and 2 times the maximum recommended human dose (MRHD) of 800 mg/day in both rats and rabbits, and an increased incidence of carpal/tarsal flexure (minor soft tissue anomaly) in rabbit fetuses at approximately 2 times the MRHD. In addition, fetal weights were decreased in both species. Maternal toxicity (observed as decreased body weights and/or death) occurred at 2 times the MRHD in rats and approximately 1-2 times the MRHD in rabbits.

The estimated background risk of major birth defects and miscarriage for the indicated populations is unknown. All pregnancies have a background risk of birth defect, loss, or other adverse outcomes. In the U.S. general population, the estimated background risk of major birth defects and miscarriage in clinically recognized pregnancies is 2 to 4% and 15 to 20%, respectively.

Clinical Considerations

Disease-associated maternal and/or fetal risk

There is a risk to the mother from untreated schizophrenia, or bipolar I disorder, including increased risk of relapse, hospitalization, and suicide. Schizophrenia and bipolar I disorder are associated with increased adverse perinatal outcomes, including preterm birth. It is not known if this is a direct result of the illness or other comorbid factors.

A prospective, longitudinal study followed 201 pregnant women with a history of major depressive disorder who were euthymic and taking antidepressants at the beginning of pregnancy. The women who discontinued antidepressants during pregnancy were more likely to experience a relapse of major depression than women who continued antidepressants. Consider the risk of untreated depression when discontinuing or changing treatment with antidepressant medication during pregnancy and postpartum.

Fetal/neonatal adverse reactions

Extrapyramidal and/or withdrawal symptoms, including agitation, hypertonia, hypotonia, tremor, somnolence, respiratory distress, and feeding disorder have been reported in neonates who were exposed to antipsychotic drugs, including SEROQUEL, during the third trimester of pregnancy. These symptoms varied in severity. Monitor neonates for extrapyramidal and/or withdrawal symptoms and manage symptoms appropriately. Some neonates recovered within hours or days without specific treatment; others required prolonged hospitalization.

Data

Human Data

Published data from observational studies, birth registries, and case reports on the use of atypical antipsychotics during pregnancy do not report a clear association with antipsychotics and major birth defects. A retrospective cohort study from a Medicaid database of 9258 women exposed to antipsychotics during pregnancy did not indicate an overall increased risk of major birth defects.

Animal Data

When pregnant rats and rabbits were exposed to quetiapine during organogenesis, there was no teratogenic effect in fetuses. Doses were 25, 50 and 200 mg/kg in rats and 25, 50 and 100 mg/kg in rabbits which are approximately 0.3, 0.6 and 2-times (rats) and 0.6, 1 and 2-times (rabbits) the MRHD for schizophrenia of 800 mg/day based on mg/m^2 body surface area. However, there was evidence of embryo-fetal toxicity including delays in skeletal ossification at approximately 1 and 2 times the MRHD of 800 mg/day in both rats and rabbits, and an increased incidence of carpal/tarsal flexure (minor soft tissue anomaly) in rabbit fetuses at approximately 2 times the MRHD. In addition, fetal weights were decreased in both species. Maternal toxicity (observed as decreased body weights and/or death) occurred at 2 times the MRHD in rats and approximately 1-2 times the MRHD (all doses tested) in rabbits.

In a peri/postnatal reproductive study in rats, no drug-related effects were observed when pregnant dams were treated with quetiapine at doses 0.01, 0.1, and 0.2 times the MRHD of 800 mg/day based on mg/m^2 body surface area. However, in a preliminary peri/postnatal study, there were increases in fetal and pup death, and decreases in mean litter weight at 3 times the MRHD.

8.2 Lactation

Risk Summary

Limited data from published literature report the presence of quetiapine in human breast milk at relative infant dose of <1% of the maternal weight-adjusted dosage. There are no consistent adverse events that have been reported in infants exposed to quetiapine through breast milk. There is no information on the effects of quetiapine on milk production. The developmental and health benefits of breastfeeding should be considered along with the mother’s clinical need for SEROQUEL and any potential adverse effects on the breastfed child from SEROQUEL or from the mother’s underlying condition.

8.3 Females and Males of Reproductive Potential

Infertility

Females

Based on the pharmacologic action of quetiapine (D2 antagonism), treatment with SEROQUEL may result in an increase in serum prolactin levels, which may lead to a reversible reduction in fertility in females of reproductive potential [see Warnings and Precautions (5.15)].

8.4 Pediatric Use

In general, the adverse reactions observed in children and adolescents during the clinical trials were similar to those in the adult population with few exceptions. Increases in systolic and diastolic blood pressure occurred in children and adolescents and did not occur in adults. Orthostatic hypotension occurred more frequently in adults (4-7%) compared to children and adolescents (< 1%) [see Warnings and Precautions (5.7) and Adverse Reactions (6.1)].

Schizophrenia

The efficacy and safety of SEROQUEL in the treatment of schizophrenia in adolescents aged 13-17 years were demonstrated in one 6-week, double-blind, placebo-controlled trial [see Indications and Usage (1.1), Dosage and Administration (2.2), Adverse Reactions (6.1), and Clinical Studies (14.1)].

Safety and effectiveness of SEROQUEL in pediatric patients less than 13 years of age with schizophrenia have not been established.

Maintenance

The safety and effectiveness of SEROQUEL in the maintenance treatment of bipolar disorder has not been established in pediatric patients less than 18 years of age. The safety and effectiveness of SEROQUEL in the maintenance treatment of schizophrenia has not been established in any patient population, including pediatric patients.

Bipolar Mania

The efficacy and safety of SEROQUEL in the treatment of mania in children and adolescents ages 10-17 years with bipolar I disorder was demonstrated in a 3-week, double-blind, placebo-controlled, multicenter trial [see Indications and Usage (1.2), Dosage and Administration (2.3), Adverse Reactions (6.1), and Clinical Studies (14.2)].

Safety and effectiveness of SEROQUEL in pediatric patients less than 10 years of age with bipolar mania have not been established.

Bipolar Depression

Safety and effectiveness of SEROQUEL in pediatric patients less than 18 years of age with bipolar depression have not been established. A clinical trial with SEROQUEL XR was conducted in children and adolescents (10-17 years of age) with bipolar depression, efficacy was not established.

Some differences in the pharmacokinetics of quetiapine were noted between children/adolescents (10-17 years of age) and adults. When adjusted for weight, the AUC and Cmax of quetiapine were 41% and 39% lower, respectively, in children and adolescents compared to adults. The pharmacokinetics of the active metabolite, norquetiapine, were similar between children/adolescents and adults after adjusting for weight [see Clinical Pharmacology (12.3)].

8.5 Geriatric Use

Of the approximately 3700 patients in clinical studies with SEROQUEL, 7% (232) were 65 years of age or over. In general, there was no indication of any different tolerability of SEROQUEL in the elderly compared to younger adults. Nevertheless, the presence of factors that might decrease pharmacokinetic clearance, increase the pharmacodynamic response to SEROQUEL, or cause poorer tolerance or orthostasis, should lead to consideration of a lower starting dose, slower titration, and careful monitoring during the initial dosing period in the elderly. The mean plasma clearance of SEROQUEL was reduced by 30% to 50% in elderly patients when compared to younger patients [see Clinical Pharmacology (12.3) and Dosage and Administration (2.3)].

8.6 Renal Impairment

Clinical experience with SEROQUEL in patients with renal impairment is limited [see Clinical Pharmacology (12.3)].

8.7 Hepatic Impairment

Since quetiapine is extensively metabolized by the liver, higher plasma levels are expected in patients with hepatic impairment. In this population, a low starting dose of 25 mg/day is recommended and the dose may be increased in increments of 25 mg/day-50 mg/day [see Dosage and Administration (2.4) and Clinical Pharmacology (12.3)].

9 DRUG ABUSE AND DEPENDENCE

9.1 Controlled Substance

SEROQUEL is not a controlled substance.

9.2 Abuse

SEROQUEL has not been systematically studied, in animals or humans, for its potential for abuse, tolerance, or physical dependence. While the clinical trials did not reveal any tendency for any drug-seeking behavior, these observations were not systematic and it is not possible to predict on the basis of this limited experience the extent to which a CNS-active drug will be misused, diverted, and/or abused once marketed. Consequently, patients should be evaluated carefully for a history of drug abuse, and such patients should be observed closely for signs of misuse or abuse of SEROQUEL, e.g., development of tolerance, increases in dose, drug-seeking behavior.

10 OVERDOSAGE

10.1 Human Experience

In clinical trials, survival has been reported in acute overdoses of up to 30 grams of quetiapine. Most patients who overdosed experienced no adverse reactions or recovered fully from the reported reactions. Death has been reported in a clinical trial following an overdose of 13.6 grams of quetiapine alone. In general, reported signs and symptoms were those resulting from an exaggeration of the drug’s known pharmacological effects, i.e., drowsiness, sedation, tachycardia, hypotension, and anticholinergic toxicity including coma and delirium. Patients with pre-existing severe cardiovascular disease may be at an increased risk of the effects of overdose [see Warnings and Precautions (5.12)]. One case, involving an estimated overdose of 9600 mg, was associated with hypokalemia and first-degree heart block. In post-marketing experience, there were cases reported of QT prolongation with overdose.

10.2 Management of Overdosage

Establish and maintain an airway and ensure adequate oxygenation and ventilation. Cardiovascular monitoring should commence immediately and should include continuous electrocardiographic monitoring to detect possible arrhythmias.

Appropriate supportive measures are the mainstay of management. For the most up-to-date information on the management of Seroquel overdosage, contact a certified Regional Poison Control Center (1-800-222-1222).

11 DESCRIPTION

SEROQUEL® (quetiapine) is an atypical antipsychotic belonging to a chemical class, the dibenzothiazepine derivatives. The chemical designation is 2-[2-(4-dibenzo [b,f] [1,4]thiazepin-11-yl-1-piperazinyl)ethoxy]-ethanol fumarate (2:1) (salt). It is present in tablets as the fumarate salt. All doses and tablet strengths are expressed as milligrams of base, not as fumarate salt. Its molecular formula is C42H50N6O4S2•C4H4O4 and it has a molecular weight of 883.11 (fumarate salt). The structural formula is:

Quetiapine fumarate is a white to off-white crystalline powder which is moderately soluble in water.

SEROQUEL is supplied for oral administration as 25 mg (round, peach), 50 mg (round, white), 100 mg (round, yellow), 200 mg (round, white), 300 mg (capsule-shaped, white), and 400 mg (capsule-shaped, yellow) tablets.

Inactive ingredients are povidone, dibasic dicalcium phosphate dihydrate, microcrystalline cellulose, sodium starch glycolate, lactose monohydrate, magnesium stearate, hypromellose, polyethylene glycol, and titanium dioxide.

The 25 mg tablets contain red ferric oxide and yellow ferric oxide and the 100 mg and 400 mg tablets contain only yellow ferric oxide.

Each 25 mg tablet contains 28.78 mg of quetiapine fumarate equivalent to 25 mg quetiapine. Each 50 mg tablet contains 57.56 mg of quetiapine fumarate equivalent to 50 mg quetiapine. Each 100 mg tablet contains 115.13 mg of quetiapine fumarate equivalent to 100 mg quetiapine. Each 200 mg tablet contains 230.26 mg of quetiapine fumarate equivalent to 200 mg quetiapine. Each 300 mg tablet contains 345.39 mg of quetiapine fumarate equivalent to 300 mg quetiapine. Each 400 mg tablet contains 460.51 mg of quetiapine fumarate equivalent to 400 mg quetiapine.

12 CLINICAL PHARMACOLOGY

12.1 Mechanism of Action

The mechanism of action of quetiapine in the listed indications is unclear. However, the efficacy of quetiapine in these indications could be mediated through a combination of dopamine type 2 (D2) and serotonin type 2 (5HT2) antagonism. The active metabolite, N-desalkyl quetiapine (norquetiapine), has similar activity at D2, but greater activity at 5HT2A receptors, than the parent drug (quetiapine).

12.2 Pharmacodynamics

Quetiapine and its metabolite, norquetiapine, have affinity for multiple neurotransmitter receptors with norquetiapine binding with higher affinity than quetiapine in general. The Ki values for quetiapine and norquetiapine at the dopamine D1 are 428/99.8 nM, at D2 626/489nM, at serotonin 5HT1A 1040/191 nM at 5HT2A 38/2.9 nM, at histamine H1 4.4/1.1 nM, at muscarinic M1 1086/38.3 nM, and at adrenergic α1b 14.6/46.4 nM and, at α2 receptors 617/1290 nM, respectively.

Quetiapine and norquetiapine lack appreciable affinity to the benzodiazepine receptors.

Effect on QT Interval

In clinical trials, quetiapine was not associated with a persistent increase in QT intervals. However, the QT effect was not systematically evaluated in a thorough QT study. In post marketing experience, there were cases reported of QT prolongation in patients who overdosed on quetiapine [see Overdosage (10.1)], in patients with concomitant illness, and in patients taking medicines known to cause electrolyte imbalance or increase QT interval.

12.3 Pharmacokinetics

Adults

Quetiapine activity is primarily due to the parent drug. The multiple-dose pharmacokinetics of quetiapine are dose-proportional within the proposed clinical dose range, and quetiapine accumulation is predictable upon multiple dosing. Elimination of quetiapine is mainly via hepatic metabolism with a mean terminal half-life of about 6 hours within the proposed clinical dose range. Steady-state concentrations are expected to be achieved within two days of dosing. Quetiapine is unlikely to interfere with the metabolism of drugs metabolized by cytochrome P450 enzymes.

Children and Adolescents

At steady state the pharmacokinetics of the parent compound, in children and adolescents (10-17 years of age), were similar to adults. However, when adjusted for dose and weight, AUC and Cmax of the parent compound were 41% and 39% lower, respectively, in children and adolescents than in adults. For the active metabolite, norquetiapine, AUC and Cmax were 45% and 31% higher, respectively, in children and adolescents than in adults. When adjusted for dose and weight, the pharmacokinetics of the metabolite, norquetiapine, was similar between children and adolescents and adults [see Use in Specific Populations (8.4)].

Absorption

Quetiapine is rapidly absorbed after oral administration, reaching peak plasma concentrations in 1.5 hours. The tablet formulation is 100% bioavailable relative to solution. The bioavailability of quetiapine is marginally affected by administration with food, with Cmax and AUC values increased by 25% and 15%, respectively.

Distribution

Quetiapine is widely distributed throughout the body with an apparent volume of distribution of 10±4 L/kg. It is 83% bound to plasma proteins at therapeutic concentrations. In vitro, quetiapine did not affect the binding of warfarin or diazepam to human serum albumin. In turn, neither warfarin nor diazepam altered the binding of quetiapine.

Metabolism and Elimination

Following a single oral dose of ^14C-quetiapine, less than 1% of the administered dose was excreted as unchanged drug, indicating that quetiapine is highly metabolized. Approximately 73% and 20% of the dose was recovered in the urine and feces, respectively.

Quetiapine is extensively metabolized by the liver. The major metabolic pathways are sulfoxidation to the sulfoxide metabolite and oxidation to the parent acid metabolite; both metabolites are pharmacologically inactive. In vitro studies using human liver microsomes revealed that the cytochrome P450 3A4 isoenzyme is involved in the metabolism of quetiapine to its major, but inactive, sulfoxide metabolite and in the metabolism of its active metabolite N-desalkyl quetiapine.

Age

Oral clearance of quetiapine was reduced by 40% in elderly patients (≥ 65 years, n=9) compared to young patients (n=12), and dosing adjustment may be necessary [see Dosage and Administration (2.3)].

Gender

There is no gender effect on the pharmacokinetics of quetiapine.

Race

There is no race effect on the pharmacokinetics of quetiapine.

Smoking

Smoking has no effect on the oral clearance of quetiapine.

Renal Insufficiency

Patients with severe renal impairment (Clcr=10-30 mL/min/1.73 m^2, n=8) had a 25% lower mean oral clearance than normal subjects (Clcr > 80 mL/min/1.73 m^2, n=8), but plasma quetiapine concentrations in the subjects with renal insufficiency were within the range of concentrations seen in normal subjects receiving the same dose. Dosage adjustment is therefore not needed in these patients [see Use in Specific Populations (8.6)].

Hepatic Insufficiency

Hepatically impaired patients (n=8) had a 30% lower mean oral clearance of quetiapine than normal subjects. In two of the 8 hepatically impaired patients, AUC and Cmax were 3 times higher than those observed typically in healthy subjects. Since quetiapine is extensively metabolized by the liver, higher plasma levels are expected in the hepatically impaired population, and dosage adjustment may be needed [see Dosage and Administration (2.4) and Use in Specific Populations (8.7)].

Drug-Drug Interaction Studies

The in vivo assessments of effect of other drugs on the pharmacokinetics of quetiapine are summarized in Table 17 [see Dosage and Administration (2.5 and 2.6) and Drug Interactions (7.1)].

Table 17: The Effect of Other Drugs on the Pharmacokinetics of Quetiapine
Coadministered Drug | Dose Schedules |  | Effect on Quetiapine Pharmacokinetics
Coadministered Drug | Coadministered Drug | Quetiapine | Effect on Quetiapine Pharmacokinetics
Phenytoin | 100 mg; three times daily | 250 mg three times daily | 5-fold increase in oral clearance
Divalproex | 500 mg; twice daily | 150 mg; twice daily | 17% increase mean max plasma concentration at steady state.; No effect on absorption or mean oral clearance
Thioridazine | 200 mg; twice daily | 300 mg; twice daily | 65% increase in oral clearance
Cimetidine | 400 mg three times daily for 4 days | 150 mg three times daily | 20% decrease in mean oral clearance
Ketoconazole (potent CYP 3A4 inhibitor) | 200 mg; once daily for 4 days | 25 mg; single dose | 84% decrease in oral clearance resulting in a 6.2-fold increase in AUC of quetiapine
Fluoxetine | 60 mg; once daily | 300 mg; twice daily | No change in steady state PK
Imipramine | 75 mg; twice daily | 300 mg; twice daily | No change in steady state PK
Haloperidol | 7.5 mg twice daily | 300 mg; twice daily | No change in steady state PK
Risperidone | 3 mg; twice daily | 300 mg; twice daily | No change in steady state PK

In vitro enzyme inhibition data suggest that quetiapine and 9 of its metabolites would have little inhibitory effect on in vivo metabolism mediated by cytochromes CYP 1A2, 2C9, 2C19, 2D6, and 3A4. Quetiapine at doses of 750 mg/day did not affect the single dose pharmacokinetics of antipyrine, lithium, or lorazepam (Table 18) [see Drug Interactions (7.2)].

Table 18: The Effect of Quetiapine on the Pharmacokinetics of Other Drugs
Coadministered drug | Dose schedules |  | Effect on other drugs pharmacokinetics
Coadministered drug | Coadministered drug | Quetiapine | Effect on other drugs pharmacokinetics
Lorazepam | 2 mg,; single dose | 250 mg; three times daily | Oral clearance of lorazepam reduced by 20%
Divalproex | 500 mg; twice daily | 150 mg; twice daily | Cmax and AUC of free valproic acid at steady-state was decreased by 10-12%
Lithium | Up to 2400 mg/day; given in twice daily doses | 250 mg; three times daily | No effect on steady-state pharmacokinetics of lithium
Antipyrine | 1 g,; single dose | 250 mg; three times daily | No effect on clearance of antipyrine or urinary recovery of its metabolites

13 NONCLINICAL TOXICOLOGY

13.1 Carcinogenesis, Mutagenesis, Impairment of Fertility

Carcinogenesis

Carcinogenicity studies were conducted in C57BL mice and Wistar rats. Quetiapine was administered in the diet to mice at doses of 20, 75, 250, and 750 mg/kg and to rats by gavage at doses of 25, 75, and 250 mg/kg for two years. These doses are equivalent to 0.1, 0.5, 1.5, and 4.5 times the MRHD of 800 mg/day based on mg/m^2 body surface area (mice) or 0.3, 1, and 3 times the MRHD based on mg/m^2 body surface area (rats). There were statistically significant increases in thyroid gland follicular adenomas in male mice at doses 1.5 and 4.5 times the MRHD based on mg/m^2 body surface area and in male rats at a dose of 3 times the MRHD on mg/m^2 body surface area. Mammary gland adenocarcinomas were statistically significantly increased in female rats at all doses tested (0.3, 1, and 3 times the MRHD based on mg/m^2 body surface area).

Thyroid follicular cell adenomas may have resulted from chronic stimulation of the thyroid gland by thyroid stimulating hormone (TSH) resulting from enhanced metabolism and clearance of thyroxine by rodent liver. Changes in TSH, thyroxine, and thyroxine clearance consistent with this mechanism were observed in subchronic toxicity studies in rat and mouse and in a 1-year toxicity study in rat; however, the results of these studies were not definitive. The relevance of the increases in thyroid follicular cell adenomas to human risk, through whatever mechanism, is unknown.

Antipsychotic drugs have been shown to chronically elevate prolactin levels in rodents. Serum measurements in a 1-year toxicity study showed that quetiapine increased median serum prolactin levels a maximum of 32- and 13-fold in male and female rats, respectively. Increases in mammary neoplasms have been found in rodents after chronic administration of other antipsychotic drugs and are considered to be prolactin-mediated. The relevance of this increased incidence of prolactin-mediated mammary gland tumors in rats to human risk is unknown [see Warnings and Precautions (5.15)].

Mutagenesis

Quetiapine was not mutagenic or clastogenic in standard genotoxicity tests. The mutagenic potential of quetiapine was tested in the in vitro Ames bacterial gene mutation assay and in the in vitro mammalian gene mutation assay in Chinese Hamster Ovary cells. The clastogenic potential of quetiapine was tested in the in vitro chromosomal aberration assay in cultured human lymphocytes and in the in vivo bone marrow micronucleus assay in rats up to 500 mg/kg, which is 6 times the MRHD based on mg/m^2 body surface area.

Impairment of Fertility

Quetiapine decreased mating and fertility in male Sprague-Dawley rats at oral doses of 50 and 150 mg/kg or approximately 1 and 3 times the MRHD of 800 mg/day based on mg/m^2 body surface area. Drug-related effects included increases in interval to mate and in the number of matings required for successful impregnation. These effects continued to be observed at 3 times the MRHD even after a two-week period without treatment. The no-effect dose for impaired mating and fertility in male rats was 25 mg/kg, or 0.3 times the MRHD based on mg/m^2 body surface area. Quetiapine adversely affected mating and fertility in female Sprague-Dawley rats at an oral dose approximately 1 times the MRHD of 800 mg/day based on mg/m^2 body surface area. Drug-related effects included decreases in matings and in matings resulting in pregnancy, and an increase in the interval to mate. An increase in irregular estrus cycles was observed at doses of 10 and 50 mg/kg, or approximately 0.1 and 1 times the MRHD of 800 mg/day based on mg/m^2 body surface area. The no-effect dose in female rats was 1 mg/kg, or 0.01 times the MRHD of 800 mg/day based on mg/m^2 body surface area.

13.2 Animal Toxicology and/or Pharmacology

Quetiapine caused a dose-related increase in pigment deposition in thyroid gland in rat toxicity studies which were 4 weeks in duration or longer and in a mouse 2-year carcinogenicity study. Doses were 10, 25, 50, 75, 150 and 250 mg/kg in rat studies which are approximately 0.1, 0.3, 0.6, 1, 2 and 3-times the MRHD of 800 mg/day based on mg/m^2 body surface area, respectively. Doses in the mouse carcinogenicity study were 20, 75, 250 and 750 mg/kg which are approximately 0.1, 0.5, 1.5, and 4.5 times the MRHD of 800 mg/day based on mg/m^2 body surface area. Pigment deposition was shown to be irreversible in rats. The identity of the pigment could not be determined, but was found to be co-localized with quetiapine in thyroid gland follicular epithelial cells. The functional effects and the relevance of this finding to human risk are unknown.

In dogs receiving quetiapine for 6 or 12 months, but not for 1-month, focal triangular cataracts occurred at the junction of posterior sutures in the outer cortex of the lens at a dose of 100 mg/kg, or 4 times the MRHD of 800 mg/day based on mg/m^2 body surface area. This finding may be due to inhibition of cholesterol biosynthesis by quetiapine. Quetiapine caused a dose-related reduction in plasma cholesterol levels in repeat-dose dog and monkey studies; however, there was no correlation between plasma cholesterol and the presence of cataracts in individual dogs. The appearance of delta-8-cholestanol in plasma is consistent with inhibition of a late stage in cholesterol biosynthesis in these species. There also was a 25% reduction in cholesterol content of the outer cortex of the lens observed in a special study in quetiapine treated female dogs. Drug-related cataracts have not been seen in any other species; however, in a 1-year study in monkeys, a striated appearance of the anterior lens surface was detected in 2/7 females at a dose of 225 mg/kg or 5.5 times the MRHD of 800 mg/day based on mg/m^2 body surface area.

14 CLINICAL STUDIES

14.1 Schizophrenia

Short-term Trials-Adults

The efficacy of SEROQUEL in the treatment of schizophrenia was established in 3 short-term (6-week) controlled trials of inpatients with schizophrenia who met DSM III-R criteria for schizophrenia. Although a single fixed dose haloperidol arm was included as a comparative treatment in one of the three trials, this single haloperidol dose group was inadequate to provide a reliable and valid comparison of SEROQUEL and haloperidol.

Several instruments were used for assessing psychiatric signs and symptoms in these studies, among them the Brief Psychiatric Rating Scale (BPRS), a multi-item inventory of general psychopathology traditionally used to evaluate the effects of drug treatment in schizophrenia. The BPRS psychosis cluster (conceptual disorganization, hallucinatory behavior, suspiciousness, and unusual thought content) is considered a particularly useful subset for assessing actively psychotic schizophrenic patients. A second traditional assessment, the Clinical Global Impression (CGI), reflects the impression of a skilled observer, fully familiar with the manifestations of schizophrenia, about the overall clinical state of the patient.

The results of the trials follow:

1. In a 6-week, placebo-controlled trial (n=361) (Study 1) involving 5 fixed doses of SEROQUEL (75 mg/day, 150 mg/day, 300 mg/day, 600 mg/day, and 750 mg/day given in divided doses three times per day), the 4 highest doses of SEROQUEL were generally superior to placebo on the BPRS total score, the BPRS psychosis cluster and the CGI severity score, with the maximal effect seen at 300 mg/day, and the effects of doses of 150 mg/day to 750 mg/day were generally indistinguishable.
2. In a 6-week, placebo-controlled trial (n=286) (Study 2) involving titration of SEROQUEL in high (up to 750 mg/day given in divided doses three times per day) and low (up to 250 mg/day given in divided doses three times per day) doses, only the high dose SEROQUEL group (mean dose, 500 mg/day) was superior to placebo on the BPRS total score, the BPRS psychosis cluster, and the CGI severity score.
3. In a 6-week dose and dose regimen comparison trial (n=618) (Study 3) involving two fixed doses of SEROQUEL (450 mg/day given in divided doses both twice daily and three times daily and 50 mg/day given in divided doses twice daily), only the 450 mg/day (225 mg given twice daily) dose group was superior to the 50 mg/day (25 mg given twice daily) SEROQUEL dose group on the BPRS total score, the BPRS psychosis cluster, and the CGI severity score.

The primary efficacy results of these three studies in the treatment of schizophrenia in adults is presented in Table 19.

Examination of population subsets (race, gender, and age) did not reveal any differential responsiveness on the basis of race or gender, with an apparently greater effect in patients under the age of 40 years compared to those older than 40. The clinical significance of this finding is unknown.

Adolescents (ages 13-17)

The efficacy of SEROQUEL in the treatment of schizophrenia in adolescents (13–17 years of age) was demonstrated in a 6-week, double-blind, placebo-controlled trial (Study 4). Patients who met DSM-IV diagnostic criteria for schizophrenia were randomized into one of three treatment groups: SEROQUEL 400 mg/day (n=73), SEROQUEL 800 mg/day (n=74), or placebo (n=75). Study medication was initiated at 50 mg/day and on day 2 increased to 100 mg/per day (divided and given two or three times per day). Subsequently, the dose was titrated to the target dose of 400 mg/day or 800 mg/day using increments of 100 mg/day, divided and given two or three times daily. The primary efficacy variable was the mean change from baseline in total Positive and Negative Syndrome Scale (PANSS).

SEROQUEL at 400 mg/day and 800 mg/day was superior to placebo in the reduction of PANSS total score. The primary efficacy results of this study in the treatment of schizophrenia in adolescents is presented in Table 19.

Table 19: Schizophrenia Short-Term Trials
Study Number | Treatment Group | Primary Efficacy Endpoint: BPRS Total
Study Number | Treatment Group | Mean Baseline; Score (SD) | LS Mean Change from Baseline (SE) | Placebo-subtracted Difference [Difference (drug minus placebo) in least-squares mean change from baseline.] (95% CI)
Study 1 | SEROQUEL (75 mg/day) | 45.7 (10.9) | -2.2 (2.0) | -4.0 (-11.2, 3.3)
Study 1 | SEROQUEL (150 mg/day) [Doses that are statistically significant superior to placebo.] | 47.2 (10.1) | -8.7 (2.1) | -10.4 (-17.8, -3.0)
Study 1 | SEROQUEL (300 mg/day) | 45.3 (10.9) | -8.6 (2.1) | -10.3 (-17.6, -3.0)
Study 1 | SEROQUEL (600 mg/day) | 43.5 (11.3) | -7.7 (2.1) | -9.4 (-16.7, -2.1)
Study 1 | SEROQUEL (750 mg/day) | 45.7 (11.0) | -6.3 (2.0) | -8.0 (-15.2, -0.8)
Study 1 | Placebo | 45.3 (9.2) | 1.7 (2.1) | --
Study 2 | SEROQUEL (250 mg/day) | 38.9 (9.8) | -4.2 (1.6) | -3.2 (-7.6, 1.2)
Study 2 | SEROQUEL (750 mg/day) | 41.0 (9.6) | -8.7 (1.6) | -7.8 (-12.2, -3.4)
Study 2 | Placebo | 38.4 (9.7) | -1.0 (1.6) | --
Study 3 | SEROQUEL (450 mg/day BID) | 42.1 (10.7) | -10.0 (1.3) | -4.6 (-7.8, -1.4)
Study 3 | SEROQUEL (450 mg/day TID) [Doses that are statistically significant superior to SEROQUEL 50 mg BID.] | 42.7 (10.4) | -8.6 (1.3) | -3.2 (-6.4, 0.0)
Study 3 | SEROQUEL (50 mg BID) | 41.7 (10.0) | -5.4 (1.3) | --
 |  | Primary Efficacy Endpoint: PANSS Total
 |  | Mean Baseline; Score (SD) | LS Mean Change; from Baseline (SE) | Placebo-subtracted; Difference (95% CI)
Study 4 | SEROQUEL (400 mg/day) | 96.2 (17.7) | -27.3 (2.6) | -8.2 (-16.1, -0.3)
Study 4 | SEROQUEL (800 mg/day) | 96.9 (15.3) | -28.4 (1.8) | -9.3 (-16.2, -2.4)
Study 4 | Placebo | 96.2 (17.7) | -19.2 (3.0) | --
SD: standard deviation; SE: standard error; LS Mean: least-squares mean; CI: unadjusted confidence interval.

14.2 Bipolar Disorder

Bipolar I disorder, manic or mixed episodes

Adults

The efficacy of SEROQUEL in the acute treatment of manic episodes was established in 3 placebo-controlled trials in patients who met DSM-IV criteria for bipolar I disorder with manic episodes. These trials included patients with or without psychotic features and excluded patients with rapid cycling and mixed episodes. Of these trials, 2 were monotherapy (12 weeks) and 1 was adjunct therapy (3 weeks) to either lithium or divalproex. Key outcomes in these trials were change from baseline in the Young Mania Rating Scale (YMRS) score at 3 and 12 weeks for monotherapy and at 3 weeks for adjunct therapy. Adjunct therapy is defined as the simultaneous initiation or subsequent administration of SEROQUEL with lithium or divalproex.

The primary rating instrument used for assessing manic symptoms in these trials was YMRS, an 11-item clinician-rated scale traditionally used to assess the degree of manic symptomatology (irritability, disruptive/aggressive behavior, sleep, elevated mood, speech, increased activity, sexual interest, language/thought disorder, thought content, appearance, and insight) in a range from 0 (no manic features) to 60 (maximum score).

The results of the trials follow:

Monotherapy

The efficacy of SEROQUEL in the acute treatment of bipolar mania was established in 2 placebo-controlled trials. In two 12-week trials (n=300, n=299) comparing SEROQUEL to placebo, SEROQUEL was superior to placebo in the reduction of the YMRS total score at weeks 3 and 12. The majority of patients in these trials taking SEROQUEL were dosed in a range between 400 mg/day and 800 mg per day (studies 1 and 2 in Table 20).

Adjunct Therapy

In this 3-week placebo-controlled trial, 170 patients with bipolar mania (YMRS ≥20) were randomized to receive SEROQUEL or placebo as adjunct treatment to lithium or divalproex. Patients may or may not have received an adequate treatment course of lithium or divalproex prior to randomization. SEROQUEL was superior to placebo when added to lithium or divalproex alone in the reduction of YMRS total score (Study 3 in Table 20).

The majority of patients in this trial taking SEROQUEL were dosed in a range between 400 mg/day and 800 mg per day. In a similarly designed trial (n=200), SEROQUEL was associated with an improvement in YMRS scores but did not demonstrate superiority to placebo, possibly due to a higher placebo effect.

The primary efficacy results of these studies in the treatment of mania in adults is presented in Table 20.

Children and Adolescents (ages 10-17)

The efficacy of SEROQUEL in the acute treatment of manic episodes associated with bipolar I disorder in children and adolescents (10-17 years of age) was demonstrated in a 3-week, double-blind, placebo-controlled, multicenter trial (Study 4 in Table 20). Patients who met DSM-IV diagnostic criteria for a manic episode were randomized into one of three treatment groups: SEROQUEL 400 mg/day (n=95), SEROQUEL 600 mg/day (n=98), or placebo (n=91). Study medication was initiated at 50 mg/day and on day 2 increased to 100 mg/day (divided doses given two or three times daily). Subsequently, the dose was titrated to a target dose of 400 mg/day or 600 mg/day using increments of 100 mg/day, given in divided doses two or three times daily. The primary efficacy variable was the mean change from baseline in total YMRS score.

SEROQUEL 400 mg/day and 600 mg/day were superior to placebo in the reduction of YMRS total score (Table 20).

Table 20: Mania Trials
Study Number | Treatment Group | Primary Efficacy Measure: YMRS Total
Study Number | Treatment Group | Mean Baseline; Score (SD) [Adult data mean baseline score is based on patients included in the primary analysis; pediatric mean baseline score is based on all patients in the ITT population.] | LS Mean Change from Baseline (SE) | Placebo-subtracted Difference [Difference (drug minus placebo) in least-squares mean change from baseline.] (95% CI)
Study 1 | SEROQUEL (200-800 mg/day) [Doses that are statistically significantly superior to placebo.] [Included in the trial as an active comparator.] | 34.0 (6.1) | -12.3 (1.3) | -4.0 (-7.0, -1.0)
Study 1 | Haloperidol | 32.3 (6.0) | -15.7 (1.3) | -7.4 (-10.4, -4.4)
Study 1 | Placebo | 33.1 (6.6) | -8.3 (1.3) | --
Study 2 | SEROQUEL (200-800 mg/day) | 32.7 (6.5) | -14.6 (1.5) | -7.9 (-10.9, -5.0)
Study 2 | Lithium | 33.3 (7.1) | -15.2 (1.6) | -8.5 (-11.5, -5.5)
Study 2 | Placebo | 34.0 (6.9) | -6.7 (1.6) | --
Study 3 | SEROQUEL (200-800 mg/day) + mood stabilizer | 31.5 (5.8) | -13.8 (1.6) | -3.8 (-7.1, -0.6)
Study 3 | Placebo + mood stabilizer | 31.1 (5.5) | -10 (1.5) | --
Study 4 | SEROQUEL (400 mg/day) | 29.4 (5.9) | -14.3 (0.96) | -5.2 (-8.1, -2.3)
Study 4 | SEROQUEL (600 mg/day) | 29.6 (6.4) | -15.6 (0.97) | -6.6 (-9.5, -3.7)
Study 4 | Placebo | 30.7 (5.9) | -9.0 (1.1) | --
Mood stabilizer: lithium or divalproex; SD: standard deviation; SE: standard error; LS Mean: least-squares mean; CI: unadjusted confidence interval.

Bipolar Disorder, Depressive Episodes

Adults

The efficacy of SEROQUEL for the acute treatment of depressive episodes associated with bipolar disorder was established in 2 identically designed 8-week, randomized, double-blind, placebo-controlled studies (N=1045) (studies 5 and 6 in Table 21). These studies included patients with either bipolar I or II disorder and those with or without a rapid cycling course. Patients randomized to SEROQUEL were administered fixed doses of either 300 mg or 600 mg once daily.

The primary rating instrument used to assess depressive symptoms in these studies was the Montgomery-Asberg Depression Rating Scale (MADRS), a 10-item clinician-rated scale with scores ranging from 0 to 60. The primary endpoint in both studies was the change from baseline in MADRS score at week 8. In both studies, SEROQUEL was superior to placebo in reduction of MADRS score. Improvement in symptoms, as measured by change in MADRS score relative to placebo, was seen in both studies at Day 8 (week 1) and onwards. In these studies, no additional benefit was seen with the 600 mg dose. For the 300 mg dose group, statistically significant improvements over placebo were seen in overall quality of life and satisfaction related to various areas of functioning, as measured using the Q-LES-Q(SF).

The primary efficacy results of these studies in the acute treatment of depressive episodes associated with bipolar disorder in adults is presented in Table 21.

Table 21: Depressive Episodes Associated with Bipolar Disorder
Study Number | Treatment Group | Primary Efficacy Measure: MADRS Total
Study Number | Treatment Group | Mean Baseline; Score (SD) | LS Mean Change from Baseline (SE) | Placebo-subtracted Difference [Difference (drug minus placebo) in least-squares mean change from baseline.] (95% CI)
Study 5 | SEROQUEL (300 mg/day) [Doses that are statistically significantly superior to placebo.] | 30.3 (5.0) | -16.4 (0.9) | -6.1 (-8.3, -3.9)
Study 5 | SEROQUEL (600 mg/day) | 30.3 (5.3) | -16.7 (0.9) | -6.5 (-8.7, -4.3)
Study 5 | Placebo | 30.6 (5.3) | -10.3 (0.9) | --
Study 6 | SEROQUEL (300 mg/day) | 31.1 (5.7) | -16.9 (1.0) | -5.0 (-7.3, -2.7)
Study 6 | SEROQUEL (600 mg/day) | 29.9 (5.6) | -16.0 (1.0) | -4.1 (-6.4, -1.8)
Study 6 | Placebo | 29.6 (5.4) | -11.9 (1.0) | --
SD: standard deviation; SE: standard error; LS Mean: least-squares mean; CI: unadjusted confidence interval.

Maintenance Treatment as an Adjunct to Lithium or Divalproex

The efficacy of SEROQUEL in the maintenance treatment of bipolar I disorder was established in 2 placebo-controlled trials in patients (n=1326) who met DSM-IV criteria for bipolar I disorder (studies 7 and 8 in Figures 1 and 2). The trials included patients whose most recent episode was manic, depressed, or mixed, with or without psychotic features. In the open-label phase, patients were required to be stable on SEROQUEL plus lithium or divalproex for at least 12 weeks in order to be randomized. On average, patients were stabilized for 15 weeks. In the randomization phase, patients continued treatment with lithium or divalproex and were randomized to receive either SEROQUEL (administered twice daily totaling 400 mg/day to 800 mg/day) or placebo. Approximately 50% of the patients had discontinued from the SEROQUEL group by day 280 and 50% of the placebo group had discontinued by day 117 of double-blind treatment. The primary endpoint in these studies was time to recurrence of a mood event (manic, mixed, or depressed episode). A mood event was defined as medication initiation or hospitalization for a mood episode; YMRS score≥20 or MADRS score≥20 at 2 consecutive assessments; or study discontinuation due to a mood event (Figure 1 and Figure 2).

In both studies, SEROQUEL was superior to placebo in increasing the time to recurrence of any mood event. The treatment effect was present for increasing time to recurrence of both manic and depressed episodes. The effect of SEROQUEL was independent of any specific subgroup (assigned mood stabilizer, sex, age, race, most recent bipolar episode, or rapid cycling course).

Figure 1: Kaplan-Meier Curves of Time to Recurrence of a Mood Event (Study 7)

Figure 2: Kaplan-Meier Curves of Time to Recurrence of a Mood Event (Study 8)

16 HOW SUPPLIED/STORAGE AND HANDLING

25 mg Tablets (NDC 0310-0275-10) peach, round, biconvex, film coated tablets, identified with ‘SEROQUEL’ and ‘25’ on one side and plain on the other side, are supplied in bottles of 100 tablets.

50 mg Tablets (NDC 0310-0278-10) white, round, biconvex, film coated tablets, identified with ‘SEROQUEL’ and ‘50’ on one side and plain on the other side, are supplied in bottles of 100 tablets.

100 mg Tablets (NDC 0310-0271-10) yellow, round, biconvex film coated tablets, identified with ‘SEROQUEL’ and ‘100’ on one side and plain on the other side, are supplied in bottles of 100 tablets.

200 mg Tablets (NDC 0310-0272-10) white, round, biconvex, film coated tablets, identified with ‘SEROQUEL’ and ‘200’ on one side and plain on the other side, are supplied in bottles of 100 tablets.

300 mg Tablets (NDC 0310-0274-60) white, capsule-shaped, biconvex, film coated tablets, intagliated with ‘SEROQUEL’ on one side and ‘300’ on the other side, are supplied in bottles of 60 tablets.

400 mg Tablets (NDC 0310-0279-10) yellow, capsule-shaped, biconvex, film coated tablets, intagliated with ‘SEROQUEL’ on one side and ‘400’ on the other side, are supplied in bottles of 100 tablets.

Store at 25ºC (77ºF); excursions permitted to 15-30ºC (59-86ºF) [See USP].

17 PATIENT COUNSELING INFORMATION

Advise the patient to read the FDA-approved patient labeling (Medication Guide).

Patients should be advised of the following issues and asked to alert their prescriber if these occur while taking SEROQUEL.

Increased Mortality in Elderly Patients with Dementia-Related Psychosis

Patients and caregivers should be advised that elderly patients with dementia-related psychosis treated with atypical antipsychotic drugs are at increased risk of death compared with placebo. Quetiapine is not approved for elderly patients with dementia-related psychosis [see Warnings and Precautions (5.1)].

Suicidal Thoughts and Behaviors

Patients, their families, and their caregivers should be encouraged to be alert to the emergence of anxiety, agitation, panic attacks, insomnia, irritability, hostility, aggressiveness, impulsivity, akathisia (psychomotor restlessness), hypomania, mania, other unusual changes in behavior, worsening of depression, and suicidal ideation, especially early during antidepressant treatment and when the dose is adjusted up or down. Families and caregivers of patients should be advised to look for the emergence of such symptoms on a day-to-day basis, since changes may be abrupt. Such symptoms should be reported to the patient's prescriber or health professional, especially if they are severe, abrupt in onset, or were not part of the patient's presenting symptoms. Symptoms such as these may be associated with an increased risk for suicidal thinking and behavior and indicate a need for very close monitoring and possibly changes in the medication [see Warnings and Precautions (5.2)].

Neuroleptic Malignant Syndrome (NMS)

Patients should be advised to report to their physician any signs or symptoms that may be related to NMS. These may include muscle stiffness and high fever [see Warnings and Precautions (5.4)].

Hyperglycemia and Diabetes Mellitus

Patients should be aware of the symptoms of hyperglycemia (high blood sugar) and diabetes mellitus. Patients who are diagnosed with diabetes, those with risk factors for diabetes, or those that develop these symptoms during treatment should have their blood glucose monitored at the beginning of and periodically during treatment [see Warnings and Precautions (5.5)].

Hyperlipidemia

Patients should be advised that elevations in total cholesterol, LDL-cholesterol and triglycerides and decreases in HDL-cholesterol may occur. Patients should have their lipid profile monitored at the beginning of and periodically during treatment [see Warnings and Precautions (5.5)].

Weight Gain

Patients should be advised that they may experience weight gain. Patients should have their weight monitored regularly [see Warnings and Precautions (5.5)].

Orthostatic Hypotension

Patients should be advised of the risk of orthostatic hypotension (symptoms include feeling dizzy or lightheaded upon standing, which may lead to falls), especially during the period of initial dose titration, and also at times of re-initiating treatment or increases in dose [see Warnings and Precautions (5.7)].

Increased Blood Pressure in Children and Adolescents

Children and adolescent patients should have their blood pressure measured at the beginning of, and periodically during, treatment [see Warnings and Precautions (5.9)].

Leukopenia/Neutropenia

Patients with a pre-existing low WBC or a history of drug induced leukopenia/neutropenia should be advised that they should have their CBC monitored while taking SEROQUEL. Patients should be advised to talk to their doctor as soon as possible if they have a fever, flu-like symptoms, sore throat, or any other infection as this could be a result of a very low WBC, which may require SEROQUEL to be stopped and/or treatment to be given [see Warnings and Precautions (5.10)].

Interference with Cognitive and Motor Performance

Patients should be advised of the risk of somnolence or sedation (which may lead to falls), especially during the period of initial dose titration. Patients should be cautioned about performing any activity requiring mental alertness, such as operating a motor vehicle (including automobiles) or operating machinery, until they are reasonably certain quetiapine therapy does not affect them adversely [see Warnings and Precautions (5.16)].

Heat Exposure and Dehydration

Patients should be advised regarding appropriate care in avoiding overheating and dehydration [see Warnings and Precautions (5.17)].

Concomitant Medication

As with other medications, patients should be advised to notify their physicians if they are taking, or plan to take, any prescription or over-the-counter drugs [see Drug Interactions (7.1)].

Pregnancy

Advise pregnant women to notify their healthcare provider if they become pregnant or intend to become pregnant during treatment with SEROQUEL. Advise patients that SEROQUEL may cause extrapyramidal and/or withdrawal symptoms (agitation, hypertonia, hypotonia, tremor, somnolence, respiratory distress, and feeding disorder) in a neonate. Advise patients that there is a pregnancy registry that monitors pregnancy outcomes in women exposed to SEROQUEL during pregnancy [see Use in Specific Populations (8.1)].

Infertility

Advise females of reproductive potential that SEROQUEL may impair fertility due to an increase in serum prolactin levels. The effects on fertility are reversible [see Use in Specific Populations (8.3)].

Need for Comprehensive Treatment Program

SEROQUEL is indicated as an integral part of a total treatment program for adolescents with schizophrenia and pediatric bipolar disorder that may include other measures (psychological, educational, and social). Effectiveness and safety of SEROQUEL have not been established in pediatric patients less than 13 years of age for schizophrenia or less than 10 years of age for bipolar mania. Appropriate educational placement is essential and psychosocial intervention is often helpful. The decision to prescribe atypical antipsychotic medication will depend upon the physician’s assessment of the chronicity and severity of the patient’s symptoms [see Indications and Usage (1.3)].

MEDICATION GUIDE

SEROQUEL (SER-oh-kwell)

(quetiapine)

Tablets

Read this Medication Guide before you start taking SEROQUEL and each time you get a refill. There may be new information. This information does not take the place of talking to your healthcare provider about your medical condition or your treatment.

What is the most important information I should know about SEROQUEL?

SEROQUEL may cause serious side effects, including:

1. risk of death in the elderly with dementia. Medicines like SEROQUEL can increase the risk of death in elderly people who have memory loss (dementia). SEROQUEL is not for treating psychosis in the elderly with dementia.
2. risk of suicidal thoughts or actions (antidepressant medicines, depression and other serious mental illnesses, and suicidal thoughts or actions).
3. Talk to your or your family member’s healthcare provider about:
  ∘ all risks and benefits of treatment with antidepressant medicines.
  ∘ all treatment choices for depression or other serious mental illness
4. Antidepressant medications may increase suicidal thoughts or actions in some children, teenagers, and young adults within the first few months of treatment.
5. Depression and other serious mental illnesses are the most important causes of suicidal thoughts and actions. Some people may have a particularly high risk of having suicidal thoughts or actions. These include people who have (or have a family history of) depression, bipolar illness (also called manic-depressive illness), or suicidal thoughts or actions.
6. How can I watch for and try to prevent suicidal thoughts and actions in myself or a family member?
  ∘ Pay close attention to any changes, especially sudden changes, in mood, behaviors, thoughts, or feelings. This is very important when an antidepressant medicine is started or when the dose is changed.
  ∘ Call the healthcare provider right away to report new or sudden changes in mood, behavior, thoughts, or feelings.
  ∘ Keep all follow-up visits with the healthcare provider as scheduled. Call the healthcare provider between visits as needed, especially if you have concerns about symptoms.

Call a healthcare provider right away if you or your family member has any of the following symptoms, especially if they are new, worse, or worry you:

- thoughts about suicide or dying
- attempts to commit suicide
- new or worse depression
- new or worse anxiety
- feeling very agitated or restless
- panic attacks
- trouble sleeping (insomnia)
- new or worse irritability
- acting aggressive, being angry, or violent
- acting on dangerous impulses
- an extreme increase in activity and talking (mania)
- other unusual changes in behavior or mood

What else do I need to know about antidepressant medicines?

- Never stop an antidepressant medicine without first talking to your healthcare provider. Stopping an antidepressant medicine suddenly can cause other symptoms.
- Antidepressants are medicines used to treat depression and other illnesses. It is important to discuss all the risks of treating depression, and also the risks of not treating it. Patients and their families or other caregivers should discuss all treatment choices with the healthcare provider, not just the use of antidepressants.
- Antidepressant medicines have other side effects. Talk to the healthcare provider about the side effects of the medicine prescribed for you or your family member.
- Antidepressant medicines can interact with other medicines. Know all of the medicines that you or your family member take. Keep a list of all medicines to show the healthcare provider. Do not start new medicines without first checking with your healthcare provider.
- Not all antidepressant medicines prescribed for children are FDA approved for use in children. Talk to your child’s healthcare provider for more information.

What is SEROQUEL?

SEROQUEL is a prescription medicine used to treat:

- schizophrenia in people 13 years of age or older
- bipolar disorder in adults, including:
  ∘ depressive episodes associated with bipolar disorder
  ∘ manic episodes associated with bipolar I disorder alone or with lithium or divalproex
  ∘ long-term treatment of bipolar I disorder with lithium or divalproex
- manic episodes associated with bipolar I disorder in children ages 10-17 years old

It is not known if SEROQUEL is safe and effective in children under 10 years of age.

What should I tell my healthcare provider before taking SEROQUEL?

Before you take SEROQUEL, tell your healthcare provider if you have or have had:

- diabetes or high blood sugar in you or your family. Your healthcare provider should check your blood sugar before you start SEROQUEL, and also during therapy
- high levels of total cholesterol, triglycerides or LDL-cholesterol, or low levels of HDL-cholesterol
- low or high blood pressure
- low white blood cell count
- cataracts
- seizures
- abnormal thyroid tests
- high prolactin levels
- heart problems
- liver problems
- any other medical condition
- pregnancy or plans to become pregnant. It is not known if SEROQUEL will harm your unborn baby.
- If you become pregnant while receiving SEROQUEL, talk to your healthcare provider about registering with the National Pregnancy Registry for Atypical Antipsychotics. You can register by calling 1-866-961-2388 or go to http://womensmentalhealth.org/clinical-and-research-programs/pregnancyregistry/
- breast-feeding or plans to breast-feed. SEROQUEL can pass into your breast milk. Talk to your healthcare provider about the best way to feed your baby if you receive SEROQUEL.
- if you have or have had a condition where you cannot completely empty your bladder (urinary retention), have an enlarged prostate, or constipation, or increased pressure inside your eyes.

Tell the healthcare provider about all the medicines that you take or recently have taken including prescription medicines, over-the-counter medicines, herbal supplements, and vitamins.

SEROQUEL and other medicines may affect each other causing serious side effects. SEROQUEL may affect the way other medicines work, and other medicines may affect how SEROQUEL works.

Tell your healthcare provider if you are having a urine drug screen because SEROQUEL may affect your test results. Tell those giving the test that you are taking SEROQUEL.

How should I take SEROQUEL?

- Take SEROQUEL exactly as your healthcare provider tells you to take it. Do not change the dose yourself.
- Take SEROQUEL by mouth, with or without food.
- If you feel you need to stop SEROQUEL, talk with your healthcare provider first. If you suddenly stop taking SEROQUEL, you may have side effects such as trouble sleeping or trouble staying asleep (insomnia), nausea, and vomiting.
- If you miss a dose of SEROQUEL, take it as soon as you remember. If you are close to your next dose, skip the missed dose. Just take the next dose at your regular time. Do not take 2 doses at the same time unless your healthcare provider tells you to. If you are not sure about your dosing, call your healthcare provider.

What should I avoid while taking SEROQUEL?

- Do not drive, operate machinery, or do other dangerous activities until you know how SEROQUEL affects you. SEROQUEL may make you drowsy.
- Avoid getting overheated or dehydrated.
  ∘ Do not over-exercise.
  ∘ In hot weather, stay inside in a cool place if possible.
  ∘ Stay out of the sun. Do not wear too much or heavy clothing.
  ∘ Drink plenty of water.
- Do not drink alcohol while taking SEROQUEL. It may make some side effects of SEROQUEL worse.

What are possible side effects of SEROQUEL?

SEROQUEL can cause serious side effects, including:

- See “What is the most important information I should know about SEROQUEL?”
- stroke that can lead to death can happen in elderly people with dementia who take medicines like SEROQUEL
- neuroleptic malignant syndrome (NMS). NMS is a rare but very serious condition that can happen in people who take antipsychotic medicines, including SEROQUEL. NMS can cause death and must be treated in a hospital. Call your healthcare provider right away if you become severely ill and have some or all of these symptoms:
  ∘ high fever
  ∘ excessive sweating
  ∘ rigid muscles
  ∘ confusion
  ∘ changes in your breathing, heartbeat, and blood pressure
- falls can happen in some people who take SEROQUEL. These falls may cause serious injuries.
- high blood sugar (hyperglycemia). High blood sugar can happen if you have diabetes already or if you have never had diabetes. High blood sugar could lead to:
  ∘ build-up of acid in your blood due to ketones (ketoacidosis)
  ∘ coma
  ∘ death
    Increases in blood sugar can happen in some people who take SEROQUEL. Extremely high blood sugar can lead to coma or death. If you have diabetes or risk factors for diabetes (such as being overweight or a family history of diabetes) your healthcare provider should check your blood sugar before you start SEROQUEL and during therapy.
    Call your healthcare provider if you have any of these symptoms of high blood sugar (hyperglycemia) while taking SEROQUEL:
  ∘ feel very thirsty
  ∘ need to urinate more than usual
  ∘ feel very hungry
  ∘ feel weak or tired
  ∘ feel sick to your stomach
  ∘ feel confused, or your breath smells fruity
- high fat levels in your blood (increased cholesterol and triglycerides). High fat levels may happen in people treated with SEROQUEL. You may not have any symptoms, so your healthcare provider may decide to check your cholesterol and triglycerides during your treatment with SEROQUEL.
- increase in weight (weight gain). Weight gain is common in people who take SEROQUEL so you and your healthcare provider should check your weight regularly. Talk to your healthcare provider about ways to control weight gain, such as eating a healthy, balanced diet, and exercising.
- movements you cannot control in your face, tongue, or other body parts (tardive dyskinesia). These may be signs of a serious condition. Tardive dyskinesia may not go away, even if you stop taking SEROQUEL. Tardive dyskinesia may also start after you stop taking SEROQUEL.
- decreased blood pressure (orthostatic hypotension), including lightheadedness or fainting caused by a sudden change in heart rate and blood pressure when rising too quickly from a sitting or lying position.
- increases in blood pressure in children and teenagers. Your healthcare provider should check blood pressure in children and adolescents before starting SEROQUEL and during therapy.
- low white blood cell count. Tell your healthcare provider as soon as possible if you have a fever, flu-like symptoms, or any other infection, as this could be a result of a very low white blood cell count. Your healthcare provider may check your white blood cell level to determine if further treatment or other action is needed.
- cataracts
- seizures
- abnormal thyroid tests. Your healthcare provider may do blood tests to check your thyroid hormone level.
- increases in prolactin levels
- sleepiness, drowsiness, feeling tired, difficulty thinking and doing normal activities
- increased body temperature
- difficulty swallowing
- trouble sleeping or trouble staying asleep (insomnia), nausea, or vomiting if you suddenly stop taking SEROQUEL. These symptoms usually get better 1 week after you start having them.

The most common side effects of SEROQUEL include:

In Adults:

- drowsiness
- sudden drop in blood pressure upon standing
- weight gain
- sluggishness
- abnormal liver tests
- upset stomach
- dry mouth
- dizziness
- weakness
- abdominal pain
- constipation
- sore throat

In Children and Adolescents:

- drowsiness
- dizziness
- fatigue
- nausea
- dry mouth
- weight gain
- increased appetite
- vomiting
- rapid heart beat

These are not all the possible side effects of SEROQUEL. For more information, ask your healthcare provider or pharmacist.

Call your doctor for medical advice about side effects. You may report side effects to FDA at 1-800-FDA-1088.

How should I store SEROQUEL?

- Store SEROQUEL at room temperature, between 68°F to 77°F (20°C to 25°C).
- Keep SEROQUEL and all medicines out of the reach of children.

General information about the safe and effective use of SEROQUEL

Medicines are sometimes prescribed for purposes other than those listed in a Medication Guide. Do not use SEROQUEL for a condition for which it was not prescribed. Do not give SEROQUEL to other people, even if they have the same symptoms you have. It may harm them.

This Medication Guide summarizes the most important information about SEROQUEL. If you would like more information, talk with your healthcare provider. You can ask your pharmacist or healthcare provider for information about SEROQUEL that is written for health professionals.

For more information, go to www.SEROQUEL.com, or call 1-800-236-9933.

What are the ingredients in SEROQUEL?

Active ingredient: quetiapine

Inactive ingredients: povidone, dibasic dicalcium phosphate dihydrate, microcrystalline cellulose, sodium starch glycolate, lactose monohydrate, magnesium stearate, hypromellose, polyethylene glycol, and titanium dioxide. The 25 mg tablets contain red and yellow ferric oxide. The 100 mg and 400 mg tablets contain only yellow ferric oxide.

This Medication Guide has been approved by the U.S. Food and Drug Administration.

SEROQUEL is a registered trademark of the AstraZeneca group of companies.

©AstraZeneca 2022

Distributed by:

AstraZeneca Pharmaceuticals LP

Wilmington, DE 19850

Revised: 01/2022

PACKAGE/LABEL PRINCIPAL DISPLAY PANEL – 25 mg

NDC 0310-0275-10 100 tablets

SeroQUEL®

(quetiapine) tablets

25 mg*

Rx only

Medication Guide must be

dispensed to patients.

AstraZeneca

PACKAGE/LABEL PRINCIPAL DISPLAY PANEL – 50 mg

NDC 0310-0278-10 100 tablets

SeroQUEL®

(quetiapine) tablets

50 mg*

Rx only

Medication Guide must be

dispensed to patients.

AstraZeneca

PACKAGE/LABEL PRINCIPAL DISPLAY PANEL – 100 mg

NDC 0310-0271-10 100 tablets

SeroQUEL®

(quetiapine) tablets

100 mg*

Rx only

Medication Guide must be

dispensed to patients.

AstraZeneca

PACKAGE/LABEL PRINCIPAL DISPLAY PANEL – 200 mg

NDC 0310-0272-10 100 tablets

SeroQUEL®

(quetiapine) tablets

200 mg*

Rx only

Medication Guide must be

dispensed to patients.

AstraZeneca

PACKAGE/LABEL PRINCIPAL DISPLAY PANEL – 300 mg

NDC 0310-0274-60 60 tablets

SeroQUEL®

(quetiapine) tablets

300 mg*

Rx only

Medication Guide must be

dispensed to patients.

AstraZeneca

PACKAGE/LABEL PRINCIPAL DISPLAY PANEL – 400 mg

NDC 0310-0279-10 100 tablets

SeroQUEL®

(quetiapine) tablets

400 mg*

Rx only

Medication Guide must be

dispensed to patients.

AstraZeneca